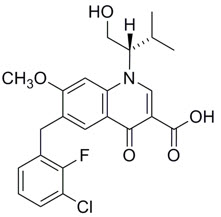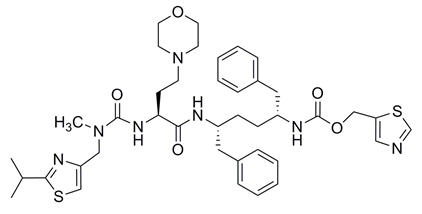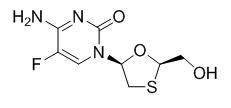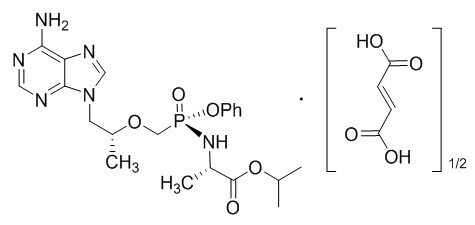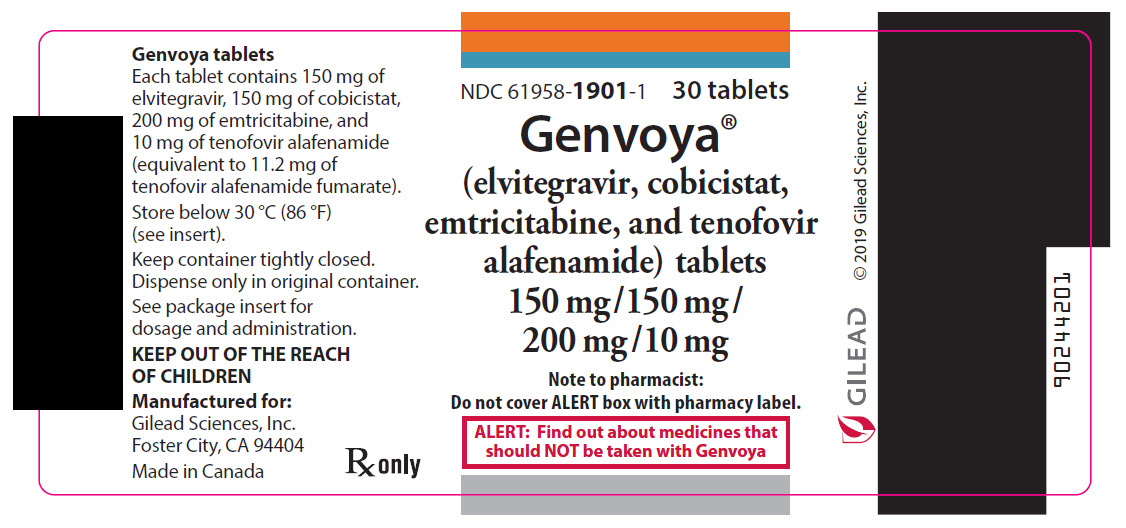 DRUG LABEL: Genvoya
NDC: 61958-1901 | Form: TABLET
Manufacturer: Gilead Sciences, Inc.
Category: prescription | Type: HUMAN PRESCRIPTION DRUG LABEL
Date: 20250203

ACTIVE INGREDIENTS: elvitegravir 150 mg/1 1; cobicistat 150 mg/1 1; emtricitabine 200 mg/1 1; tenofovir alafenamide fumarate 10 mg/1 1
INACTIVE INGREDIENTS: LACTOSE MONOHYDRATE; MICROCRYSTALLINE CELLULOSE; HYDROXYPROPYL CELLULOSE (1600000 WAMW); SODIUM LAURYL SULFATE; CROSCARMELLOSE SODIUM; WATER; MAGNESIUM STEARATE; POLYVINYL ALCOHOL, UNSPECIFIED; TITANIUM DIOXIDE; POLYETHYLENE GLYCOL, UNSPECIFIED; TALC; FD&C BLUE NO. 2; FERRIC OXIDE YELLOW

HIGHLIGHTS OF PRESCRIBING INFORMATION

These highlights do not include all the information needed to use GENVOYA safely and effectively. See full prescribing information for GENVOYA.
GENVOYA® (elvitegravir, cobicistat, emtricitabine, and tenofovir alafenamide) tablets, for oral use
Initial U.S. Approval: 2015

WARNING: POST TREATMENT ACUTE EXACERBATION OF HEPATITIS B

See full prescribing information for complete boxed warning.

Severe acute exacerbations of hepatitis B have been reported in patients who are coinfected with HIV-1 and HBV and have discontinued products containing emtricitabine and/or tenofovir disoproxil fumarate (TDF), and may occur with discontinuation of GENVOYA. Hepatic function should be monitored closely in these patients. If appropriate, anti-hepatitis B therapy may be warranted. (5.1)

RECENT MAJOR CHANGES

Warnings and Precautions, New Onset or Worsening Renal Impairment (5.4) | 03/2021

1 INDICATIONS AND USAGE

GENVOYA is a four-drug combination of elvitegravir (EVG), an HIV-1 integrase strand transfer inhibitor (INSTI), cobicistat (COBI), a CYP3A inhibitor, and emtricitabine (FTC) and tenofovir alafenamide (TAF), both HIV-1 nucleoside analog reverse transcriptase inhibitors (NRTIs), and is indicated as a complete regimen for the treatment of HIV-1 infection in adults and pediatric patients weighing at least 25 kg who have no antiretroviral treatment history or to replace the current antiretroviral regimen in those who are virologically-suppressed (HIV-1 RNA less than 50 copies per mL) on a stable antiretroviral regimen for at least 6 months with no history of treatment failure and no known substitutions associated with resistance to the individual components of GENVOYA. (1)

2 DOSAGE AND ADMINISTRATION

- Testing: Prior to or when initiating GENVOYA test for hepatitis B virus infection. Prior to or when initiating GENVOYA, and during treatment on a clinically appropriate schedule, assess serum creatinine, estimated creatinine clearance, urine glucose, and urine protein in all patients. In patients with chronic kidney disease, also assess serum phosphorus. (2.1)
- Recommended dosage in adult and pediatric patients weighing at least 25 kg: One tablet taken orally once daily with food in patients with body weight at least 25 kg and a creatinine clearance greater than or equal to 30 mL per minute, or in adult patients with creatinine clearance less than 15 mL per minute who are receiving chronic hemodialysis. On days of hemodialysis, administer GENVOYA after hemodialysis. (2.2)
- Renal impairment: GENVOYA is not recommended in patients with estimated creatinine clearance of 15 to below 30 mL per minute, or below 15 mL per minute who are not receiving chronic hemodialysis. (2.3)
- Hepatic impairment: GENVOYA is not recommended in patients with severe hepatic impairment. (2.4)

3 DOSAGE FORMS AND STRENGTHS

Tablets: 150 mg of elvitegravir, 150 mg of cobicistat, 200 mg of emtricitabine, and 10 mg of tenofovir alafenamide. (3)

4 CONTRAINDICATIONS

Coadministration of GENVOYA is contraindicated with drugs that:

- Are highly dependent on CYP3A for clearance and for which elevated plasma concentrations are associated with serious adverse events. (4)
- Strongly induce CYP3A, which may lead to lower exposure of one or more components and loss of efficacy of GENVOYA and possible resistance. (4)

5 WARNINGS AND PRECAUTIONS

- Risk of adverse reactions or loss of virologic response due to drug interactions: The concomitant use of GENVOYA and other drugs may result in known or potentially significant drug interactions, some of which may lead to loss of therapeutic effect of GENVOYA and possible development of resistance; clinically significant adverse reactions from greater exposures of concomitant drugs; or loss of therapeutic effect of concomitant drugs. (5.2)
- Immune reconstitution syndrome: May necessitate further evaluation and treatment. (5.3)
- New onset or worsening renal impairment: Assess serum creatinine, estimated creatinine clearance, urine glucose and urine protein when initiating GENVOYA and during therapy on a clinically appropriate schedule in all patients. Also assess serum phosphorus in patients with chronic kidney disease. (5.4)
- Lactic acidosis/severe hepatomegaly with steatosis: Discontinue treatment in patients who develop symptoms or laboratory findings suggestive of lactic acidosis or pronounced hepatotoxicity. (5.5)

6 ADVERSE REACTIONS

Most common adverse reaction (incidence greater than or equal to 10%, all grades) is nausea. (6.1)

To report SUSPECTED ADVERSE REACTIONS, contact Gilead Sciences, Inc. at 1-800-GILEAD-5 or FDA at 1-800-FDA-1088 or www.fda.gov/medwatch.

7 DRUG INTERACTIONS

- GENVOYA should not be administered with other antiretroviral medications for treatment of HIV-1 infection. (7.1)
- GENVOYA can alter the concentration of drugs metabolized by CYP3A or CYP2D6. Drugs that induce CYP3A can alter the concentrations of one or more components of GENVOYA. Consult the full prescribing information prior to and during treatment for potential drug-drug interactions. (4, 7.2, 7.3, 12.3)

8 USE IN SPECIFIC POPULATIONS

- Pregnancy: Not recommended for use during pregnancy because of substantially lower exposures of cobicistat and elvitegravir during pregnancy. GENVOYA should not be initiated in pregnant individuals. (2.5, 8.1)
- Lactation: Breastfeeding is not recommended due to the potential for HIV transmission. (8.2)
- Pediatrics: Not recommended for patients weighing less than 25 kg. (8.4)

FULL PRESCRIBING INFORMATION

WARNING: POST TREATMENT ACUTE EXACERBATION OF HEPATITIS B

Severe acute exacerbations of hepatitis B have been reported in patients who are coinfected with HIV-1 and HBV and have discontinued products containing emtricitabine and/or tenofovir disoproxil fumarate (TDF), and may occur with discontinuation of GENVOYA. Hepatic function should be monitored closely with both clinical and laboratory follow-up for at least several months in patients who are coinfected with HIV-1 and HBV and discontinue GENVOYA. If appropriate, anti-hepatitis B therapy may be warranted [see Warnings and Precautions (5.1)].

1 INDICATIONS AND USAGE

GENVOYA is indicated as a complete regimen for the treatment of HIV-1 infection in adults and pediatric patients weighing at least 25 kg who have no antiretroviral treatment history or to replace the current antiretroviral regimen in those who are virologically-suppressed (HIV-1 RNA less than 50 copies per mL) on a stable antiretroviral regimen for at least 6 months with no history of treatment failure and no known substitutions associated with resistance to the individual components of GENVOYA [see Clinical Studies (14)].

2 DOSAGE AND ADMINISTRATION

2.1 Testing When Initiating and During Treatment with GENVOYA

Prior to or when initiating GENVOYA, test patients for hepatitis B virus infection [see Warnings and Precautions (5.1)].

Prior to or when initiating GENVOYA, and during treatment with GENVOYA on a clinically appropriate schedule, assess serum creatinine, estimated creatinine clearance, urine glucose and urine protein in all patients. In patients with chronic kidney disease, also assess serum phosphorus [see Warnings and Precautions (5.4)].

2.2 Recommended Dosage in Adults and Pediatric Patients Weighing at Least 25 kg

GENVOYA is a four-drug fixed dose combination product containing elvitegravir (EVG), cobicistat (COBI), emtricitabine (FTC), and tenofovir alafenamide (TAF). The recommended dosage of GENVOYA is one tablet containing 150 mg EVG,150 mg COBI, 200 mg FTC, and 10 mg TAF taken orally once daily with food in:

- adults and pediatric patients with body weight at least 25 kg and creatinine clearance greater than or equal to 30 mL per minute; or
- adults with creatinine clearance below 15 mL per minute who are receiving chronic hemodialysis. On days of hemodialysis, administer GENVOYA after completion of hemodialysis treatment [see Use in Specific Populations (8.6) and Clinical Pharmacology (12.3)].

2.3 Not Recommended in Patients with Severe Renal Impairment

GENVOYA is not recommended in patients with:

- severe renal impairment (estimated creatinine clearance of 15 to below 30 mL per minute); or
- end stage renal disease (ESRD; estimated creatinine clearance below 15 mL per minute) who are not receiving chronic hemodialysis [see Dosage and Administration (2.2) and Use in Specific Populations (8.6)].

2.4 Not Recommended in Patients with Severe Hepatic Impairment

GENVOYA is not recommended in patients with severe hepatic impairment (Child-Pugh Class C) [see Use in Specific Populations (8.7) and Clinical Pharmacology (12.3)].

2.5 Not Recommended During Pregnancy

GENVOYA is not recommended for use during pregnancy because of substantially lower exposures of cobicistat and elvitegravir during the second and third trimesters [see Use in Specific Populations (8.1)].

GENVOYA should not be initiated in pregnant individuals. An alternative regimen is recommended for individuals who become pregnant during therapy with GENVOYA [see Use in Specific Populations (8.1)].

3 DOSAGE FORMS AND STRENGTHS

Each GENVOYA tablet contains 150 mg of elvitegravir (EVG), 150 mg of cobicistat (COBI), 200 mg of emtricitabine (FTC), and 10 mg of tenofovir alafenamide (TAF) (equivalent to 11.2 mg of tenofovir alafenamide fumarate).

The tablets are green, capsule-shaped, film-coated tablets, debossed with "GSI" on one side of the tablet and the number "510" on the other side of the tablet.

4 CONTRAINDICATIONS

Coadministration of GENVOYA is contraindicated with drugs that are highly dependent on CYP3A for clearance and for which elevated plasma concentrations are associated with serious and/or life-threatening events. These drugs and other contraindicated drugs (which may lead to reduced efficacy of GENVOYA and possible resistance) are listed below [see Drug Interactions (7.5) and Clinical Pharmacology (12.3)].

- Alpha 1-adrenoreceptor antagonist: alfuzosin
- Anticonvulsants: carbamazepine, phenobarbital, phenytoin
- Antimycobacterial: rifampin
- Antipsychotics: lurasidone, pimozide
- Ergot Derivatives: dihydroergotamine, ergotamine, methylergonovine
- Herbal Products: St. John's wort (Hypericum perforatum)
- Lipid-modifying Agents: lomitapide, lovastatin, simvastatin
- Phosphodiesterase-5 (PDE-5) Inhibitor: sildenafil when administered as REVATIO® for the treatment of pulmonary arterial hypertension
- Sedative/hypnotics: triazolam, orally administered midazolam

5 WARNINGS AND PRECAUTIONS

5.1 Severe Acute Exacerbation of Hepatitis B in Patients Coinfected with HIV-1 and HBV

Patients with HIV-1 should be tested for the presence of hepatitis B virus (HBV) before or when initiating antiretroviral therapy [see Dosage and Administration (2.1)].

Severe acute exacerbations of hepatitis B (e.g., liver decompensation and liver failure) have been reported in patients who are coinfected with HIV-1 and HBV and have discontinued products containing emtricitabine and/or tenofovir disoproxil fumarate (TDF), and may occur with discontinuation of GENVOYA. Patients coinfected with HIV-1 and HBV who discontinue GENVOYA should be closely monitored with both clinical and laboratory follow-up for at least several months after stopping treatment. If appropriate, anti-hepatitis B therapy may be warranted, especially in patients with advanced liver disease or cirrhosis, since post-treatment exacerbation of hepatitis may lead to hepatic decompensation and liver failure.

5.2 Risk of Adverse Reactions or Loss of Virologic Response Due to Drug Interactions

The concomitant use of GENVOYA and other drugs may result in known or potentially significant drug interactions, some of which may lead to [see Contraindications (4) and Drug Interactions (7.5)]:

- Loss of therapeutic effect of GENVOYA and possible development of resistance.
- Clinically significant adverse reactions, potentially leading to severe, life-threatening, or fatal events, from greater exposures of concomitant drugs metabolized by CYP3A.
- Loss of therapeutic effect of concomitant drugs that utilize CYP3A to form active metabolites.

See Table 5 for steps to prevent or manage these possible and known significant drug interactions, including dosing recommendations [see Drug Interactions (7)]. Consider the potential for drug interactions prior to and during GENVOYA therapy; review concomitant medications during GENVOYA therapy; and monitor for the adverse reactions associated with the concomitant drugs.

5.3 Immune Reconstitution Syndrome

Immune reconstitution syndrome has been reported in patients treated with combination antiretroviral therapy, including emtricitabine, a component of GENVOYA. During the initial phase of combination antiretroviral treatment, patients whose immune system responds may develop an inflammatory response to indolent or residual opportunistic infections [such as Mycobacterium avium infection, cytomegalovirus, Pneumocystis jirovecii pneumonia (PCP), or tuberculosis], which may necessitate further evaluation and treatment.

Autoimmune disorders (such as Graves' disease, polymyositis, Guillain-Barré syndrome, and autoimmune hepatitis) have also been reported to occur in the setting of immune reconstitution, however, the time to onset is more variable, and can occur many months after initiation of treatment.

5.4 New Onset or Worsening Renal Impairment

Postmarketing cases of renal impairment, including acute renal failure, proximal renal tubulopathy (PRT), and Fanconi syndrome have been reported with TAF-containing products; while most of these cases were characterized by potential confounders that may have contributed to the reported renal events, it is also possible these factors may have predisposed patients to tenofovir-related adverse events [see Adverse Reactions (6.1, 6.2)]. GENVOYA is not recommended in patients with estimated creatinine clearance of 15 to below 30 mL per minute, or in patients with estimated creatinine clearance below 15 mL per minute who are not receiving chronic hemodialysis.

Patients taking tenofovir prodrugs who have impaired renal function and those taking nephrotoxic agents including non-steroidal anti-inflammatory drugs are at increased risk of developing renal-related adverse reactions.

Prior to or when initiating GENVOYA, and during treatment with GENVOYA on a clinically appropriate schedule, assess serum creatinine, estimated creatinine clearance, urine glucose and urine protein in all patients. In patients with chronic kidney disease, also assess serum phosphorus. Discontinue GENVOYA in patients who develop clinically significant decreases in renal function or evidence of Fanconi syndrome.

Cobicistat, a component of GENVOYA, produces elevations of serum creatinine due to inhibition of tubular secretion of creatinine without affecting glomerular filtration [see Adverse Reactions (6.1)]. The elevation is typically seen within 2 weeks of starting therapy and is reversible after discontinuation. Patients who experience a confirmed increase in serum creatinine of greater than 0.4 mg per dL from baseline should be closely monitored for renal safety.

5.5 Lactic Acidosis/Severe Hepatomegaly with Steatosis

Lactic acidosis and severe hepatomegaly with steatosis, including fatal cases, have been reported with the use of nucleoside analogs, including emtricitabine, a component of GENVOYA, and tenofovir DF, another prodrug of tenofovir, alone or in combination with other antiretrovirals. Treatment with GENVOYA should be suspended in any patient who develops clinical or laboratory findings suggestive of lactic acidosis or pronounced hepatotoxicity (which may include hepatomegaly and steatosis even in the absence of marked transaminase elevations).

6 ADVERSE REACTIONS

The following adverse drug reactions are discussed in other sections of the labeling:

- Severe Acute Exacerbations of Hepatitis B [see Warnings and Precautions (5.1)]
- Immune Reconstitution Syndrome [see Warnings and Precautions (5.3)]
- New Onset or Worsening Renal Impairment [see Warnings and Precautions (5.4)]
- Lactic Acidosis/Severe Hepatomegaly with Steatosis [see Warnings and Precautions (5.5)]

6.1 Clinical Trials Experience

Because clinical trials are conducted under widely varying conditions, adverse reaction rates observed in the clinical trials of a drug cannot be directly compared to rates in the clinical trials of another drug and may not reflect the rates observed in practice.

Clinical Trials in Treatment-Naïve Adults

The primary safety assessment of GENVOYA was based on Week 144 pooled data from 1,733 subjects in two randomized, double-blind, active-controlled trials, Study 104 and Study 111, in antiretroviral treatment-naïve HIV-1 infected adult subjects. A total of 866 subjects received one tablet of GENVOYA once daily [see Clinical Studies (14.2)].

The most common adverse reaction (all Grades) reported in at least 10% of subjects in the GENVOYA group was nausea. The proportion of subjects who discontinued treatment with GENVOYA or STRIBILD® due to adverse events, regardless of severity, was 1% and 2%, respectively. Table 1 displays the frequency of adverse reactions (all Grades) greater than or equal to 5% in the GENVOYA group.

Table 1 Adverse Reactions [Frequencies of adverse reactions are based on all adverse events attributed to study drugs by the investigator.] (All Grades) Reported in ≥ 5% of HIV-1 Infected Treatment-Naïve Adults Receiving GENVOYA in Studies 104 and 111 (Week 144 analysis)
 | GENVOYA N=866 | STRIBILD N=867
Nausea | 11% | 13%
Diarrhea | 7% | 9%
Headache | 6% | 5%
Fatigue | 5% | 4%

The majority of events presented in Table 1 occurred at severity Grade 1.

Clinical Trials in Virologically Suppressed Adults

The safety of GENVOYA in virologically-suppressed adults was based on Week 96 data from 959 subjects in a randomized, open-label, active-controlled trial (Study 109) in which virologically-suppressed subjects were switched from a TDF-containing combination regimen to GENVOYA. Overall, the safety profile of GENVOYA in subjects in this study was similar to that of treatment-naïve subjects [see Clinical Studies (14.3)]. Additional adverse reactions observed with GENVOYA in Study 109 included suicidal ideation, suicidal behavior, and suicide attempt (<1% combined); all of these events were serious and all occurred in subjects with a preexisting history of depression or psychiatric illness.

Clinical Trials in Adult Subjects with Renal Impairment

In an open-label trial (Study 112), 248 HIV-1 infected subjects with estimated creatinine clearance between 30 and 69 mL per minute (by Cockcroft-Gault method) were treated with GENVOYA for a median duration of 144 weeks. Of these subjects, 65% had previously been on a stable TDF-containing regimen. A total of 5 subjects permanently discontinued GENVOYA due to the development of renal adverse events through Week 96. Three of these five were among the 80 subjects with baseline estimated creatinine clearance of less than 50 mL/min and two subjects were among the 162 subjects with baseline estimated creatinine clearance of greater than or equal to 50 mL/min. There were no further renal discontinuations between Weeks 96 and 144. Overall, renally impaired subjects receiving GENVOYA in this study had a mean serum creatinine of 1.5 mg/dL at baseline and 1.4 mg/dL at Week 144. Otherwise, the safety profile of GENVOYA in subjects in this study was similar to that of subjects with normal renal function.

Virologically-Suppressed Adults with End Stage Renal Disease (ESRD) Receiving Chronic Hemodialysis

The safety of GENVOYA in subjects with end stage renal disease (ESRD) (estimated creatinine clearance of less than 15 mL/min) on chronic hemodialysis was assessed in 55 subjects (Study 1825) [see Clinical Studies (14.4)]. The most commonly reported adverse reaction (adverse event assessed as causally related by investigator and all grades) was nausea (7%). Serious adverse events were reported in 53% of subjects and the most common serious adverse events were pneumonia (13%), fluid overload (7%), hyperkalemia (7%) and osteomyelitis (7%). Overall 5% of subjects permanently discontinued treatment due to an adverse event.

Renal Laboratory Tests and Renal Safety

Treatment-Naïve Adults:

Cobicistat (a component of GENVOYA) has been shown to increase serum creatinine due to inhibition of tubular secretion of creatinine without affecting glomerular filtration [see Clinical Pharmacology (12.2)]. Increases in serum creatinine occurred by Week 2 of treatment and remained stable through 144 weeks.

In two 144-week randomized, controlled trials in a total of 1,733 treatment-naïve adults with a median baseline estimated creatinine clearance of 115 mL per minute, mean serum creatinine increased by less than 0.1 mg per dL in the GENVOYA group and by 0.1 mg per dL in the STRIBILD group from baseline to Week 144.

Virologically Suppressed Adults:

In a study of 1,436 virologically-suppressed TDF-treated adults with a mean baseline estimated creatinine clearance of 112 mL per minute who were randomized to continue their treatment regimen or switch to GENVOYA, at Week 96 mean serum creatinine was similar to baseline for both those continuing baseline treatment and those switching to GENVOYA.

Across these trials, renal serious adverse events or discontinuations due to renal adverse reactions were encountered in less than 1% of participants treated with GENVOYA.

Bone Mineral Density Effects

Treatment-Naïve Adults:

In a pooled analysis of Studies 104 and 111, the effects of GENVOYA compared to STRIBILD on bone mineral density (BMD) change from baseline to Week 144 were assessed by dual-energy X-ray absorptiometry (DXA). The mean percentage change in BMD from baseline to Week 144 was −0.92% with GENVOYA compared to −2.95% with STRIBILD at the lumbar spine and −0.75% compared to −3.36% at the total hip. BMD declines of 5% or greater at the lumbar spine were experienced by 15% of GENVOYA subjects and 29% of STRIBILD subjects. BMD declines of 7% or greater at the femoral neck were experienced by 15% of GENVOYA subjects and 29% of STRIBILD subjects. The long-term clinical significance of these BMD changes is not known.

Virologically Suppressed Adults:

In Study 109, TDF-treated subjects were randomized to continue their TDF-based regimen or switch to GENVOYA; changes in BMD from baseline to Week 96 were assessed by DXA. Mean BMD increased in subjects who switched to GENVOYA (2.12% lumbar spine, 2.44% total hip) and decreased slightly in subjects who continued their baseline regimen (−0.09% lumbar spine, −0.46% total hip). BMD declines of 5% or greater at the lumbar spine were experienced by 2% of GENVOYA subjects and 6% of subjects who continued their TDF-based regimen. BMD declines of 7% or greater at the femoral neck were experienced by 2% of GENVOYA subjects and 7% of subjects who continued their TDF-based regimen. The long-term clinical significance of these BMD changes is not known.

Laboratory Abnormalities:

The frequency of laboratory abnormalities (Grades 3–4) occurring in at least 2% of subjects receiving GENVOYA in Studies 104 and 111 are presented in Table 2.

Table 2 Laboratory Abnormalities (Grades 3–4) Reported in ≥ 2% of Subjects Receiving GENVOYA in Studies 104 and 111 (Week 144 analysis)
Laboratory Parameter Abnormality [Frequencies are based on treatment-emergent laboratory abnormalities.] | GENVOYA N=866 | STRIBILD N=867
Creatine Kinase (≥10.0 × ULN) | 11% | 10%
LDL-cholesterol (fasted) (>190 mg/dL) | 11% | 5%
Total cholesterol (fasted) (>300mg/dL) | 4% | 3%
Amylase | 3% | 5%
ALT | 3% | 3%
AST | 3% | 4%
Urine RBC (Hematuria) (>75 RBC/HPF) | 3% | 3%

Serum Lipids:

Subjects receiving GENVOYA experienced greater increases in serum lipids compared to those receiving STRIBILD.

Changes from baseline in total cholesterol, HDL-cholesterol, LDL-cholesterol, triglycerides and total cholesterol to HDL ratio are presented in Table 3.

Table 3 Lipid Values, Mean Change from Baseline, Reported in Subjects Receiving GENVOYA or STRIBILD in Trials 104 and 111 [Excludes subjects who received lipid lowering agents during the treatment period.]
 | GENVOYA N=866 |  | STRIBILD N=867
 | Baseline | Week 144 | Baseline | Week 144
 | mg/dL | Change [The change from baseline is the mean of within-subject changes from baseline for subjects with both baseline and Week 144 values.] | mg/dL | Change
Total Cholesterol (fasted) | 162 [N=647] | +31 [N=647] | 165 [N=627] | +14 [N=627]
Triglycerides (fasted) | 111 [N=647] | +29 [N=647] | 115 [N=627] | +17 [N=627]
LDL-cholesterol (fasted) | 103 [N=647] | +20 [N=643] | 107 [N=628] | +8 [N=628]
HDL-cholesterol (fasted) | 47 [N=647] | +7 [N=647] | 46 [N=627] | +3 [N=627]
Total Cholesterol to HDL ratio | 3.7 [N=647] | 0.2 [N=647] | 3.8 [N=627] | 0.1 [N=627]

Clinical Trials in Pediatric Subjects:

Safety in Pediatric Patients

The safety of GENVOYA in HIV-1 infected pediatric subjects was evaluated in treatment-naïve subjects between the ages of 12 to less than 18 years and weighing at least 35 kg (N=50) through Week 48 (cohort 1), and in virologically-suppressed subjects between the ages of 6 to less than 12 years and weighing at least 25 kg (N=52) through Week 48 (cohort 2) in an open-label clinical trial (Study 106) [see Clinical Studies (14.5)]. With the exception of a decrease in the mean CD4+ cell count observed in cohort 2 of Study 106, the safety profile in pediatric subjects who received treatment with GENVOYA was similar to that in adults. One 13-year-old female subject developed unexplained uveitis while receiving GENVOYA that resolved and did not require discontinuation of GENVOYA.

Bone Mineral Density Effects

Cohort 1: Treatment-naïve adolescents (12 to less than 18 years; at least 35 kg)

Among the subjects in cohort 1 receiving GENVOYA, mean BMD increased from baseline to Week 48, + 4.2% at the lumbar spine and + 1.3% for the total body less head (TBLH). Mean changes from baseline BMD Z-scores were −0.07 for lumbar spine and −0.20 for TBLH at Week 48. One GENVOYA subject had significant (at least 4%) lumbar spine BMD loss at Week 48.

Cohort 2: Virologically-suppressed children (6 to less than 12 years; at least 25 kg)

Among the subjects in cohort 2 receiving GENVOYA, mean BMD increased from baseline to Week 48, +3.9% at the lumbar spine and +4.2% for TBLH. Mean changes from baseline BMD Z-scores were -0.24 for lumbar spine and -0.19 for TBLH at Week 48. Six GENVOYA subjects had significant (at least 4%) lumbar spine BMD loss at Week 48; 2 subjects also had at least 4% TBLH BMD loss at Week 48.

Change from Baseline in CD4+ cell counts

Cohort 2: Virologically-suppressed children (6 to less than 12 years; at least 25 kg)

Cohort 2 of Study 106 evaluated pediatric subjects (N=52) who were virologically-suppressed and who switched from their antiretroviral regimen to GENVOYA. Although all subjects had HIV-1 RNA < 50 copies/mL, there was a decrease from baseline in CD4+ cell count at Weeks 24 and 48. The mean baseline and mean change from baseline in CD4+ cell count and in CD4% from Week 2 to Week 48 are presented in Table 4. All subjects maintained their CD4+ cell counts above 400 cells/mm^3 [see Pediatric Use (8.4) and Clinical Studies (14.5)].

Table 4 Mean Change in CD4+ Count and CD4 Percentage from Baseline to Week 48 in Virologically-Suppressed Pediatric Patients from 6 to <12 Years Who Switched to GENVOYA
 | Baseline | Mean Change from Baseline
 | Baseline | Week 2 | Week 4 | Week 12 | Week 24 | Week 32 | Week 48
CD4+ Cell Count (cells/mm^3) | 961 (275.5) [Mean (SD)] | -117 | -114 | -112 | -118 | -62 | -66
CD4% | 38 (6.4) | +0.3% | -0.1% | -0.8% | -0.8% | -1.0% | -0.6%

6.2 Postmarketing Experience

The following events have been identified during post approval use of products containing TAF, including GENVOYA. Because these events are reported voluntarily from a population of uncertain size, it is not always possible to reliably estimate their frequency or establish a causal relationship to drug exposure.

Skin and Subcutaneous Tissue Disorders

Angioedema, urticaria, and rash

Renal and Urinary Disorders

Acute renal failure, acute tubular necrosis, proximal renal tubulopathy, and Fanconi syndrome

7 DRUG INTERACTIONS

7.1 Not Recommended with Other Antiretroviral Medications

GENVOYA is a complete regimen for the treatment of HIV-1 infection; therefore, coadministration of GENVOYA with other antiretroviral medications for treatment of HIV-1 infection should be avoided. Complete information regarding potential drug-drug interactions with other antiretroviral medications is not provided [see Contraindications (4), Warnings and Precautions (5.2) and Clinical Pharmacology (12.3)].

7.2 Potential for GENVOYA to Affect Other Drugs

Cobicistat, a component of GENVOYA, is an inhibitor of CYP3A and CYP2D6 and an inhibitor of the following transporters: P-glycoprotein (P-gp), BCRP, OATP1B1 and OATP1B3. Thus, coadministration of GENVOYA with drugs that are primarily metabolized by CYP3A or CYP2D6, or are substrates of P-gp, BCRP, OATP1B1 or OATP1B3 may result in increased plasma concentrations of such drugs . Coadministration of GENVOYA with drugs that have active metabolite(s) formed by CYP3A may result in reduced plasma concentration of these active metabolite(s) (see Table 5). Elvitegravir is a modest inducer of CYP2C9 and may decrease the plasma concentrations of CYP2C9 substrates. TAF is not an inhibitor of CYP1A2, CYP2B6, CYP2C8, CYP2C9, CYP2C19, CYP2D6, or UGT1A1. TAF is a weak inhibitor of CYP3A in vitro. TAF is not an inhibitor or inducer of CYP3A in vivo.

7.3 Potential for Other Drugs to Affect One or More Components of GENVOYA

Elvitegravir and cobicistat, components of GENVOYA, are metabolized by CYP3A. Cobicistat is also metabolized, to a minor extent, by CYP2D6.

Drugs that induce CYP3A activity are expected to increase the clearance of elvitegravir and cobicistat, resulting in decreased plasma concentration of cobicistat, elvitegravir, and TAF, which may lead to loss of therapeutic effect of GENVOYA and development of resistance (see Table 5).

Coadministration of GENVOYA with other drugs that inhibit CYP3A may decrease the clearance and increase the plasma concentration of cobicistat. (see Table 5). TAF, a component of GENVOYA, is a substrate of P-gp, BCRP, OATP1B1 and OATP1B3. Drugs that inhibit P-gp and/or BCRP, such as cobicistat, may increase the absorption of TAF (see Table 13). However, when TAF is administered as a component of GENVOYA, its availability is increased by cobicistat and a further increase of TAF concentrations is not expected upon coadministration of an additional P-gp and/or BCRP inhibitor. Drugs that induce P-gp activity are expected to decrease the absorption of TAF, resulting in decreased plasma concentration of TAF.

7.4 Drugs Affecting Renal Function

Because emtricitabine and tenofovir are primarily excreted by the kidneys by a combination of glomerular filtration and active tubular secretion, coadministration of GENVOYA with drugs that reduce renal function or compete for active tubular secretion may increase concentrations of emtricitabine, tenofovir, and other renally eliminated drugs and this may increase the risk of adverse reactions. Some examples of drugs that are eliminated by active tubular secretion include, but are not limited to, acyclovir, cidofovir, ganciclovir, valacyclovir, valganciclovir, aminoglycosides (e.g., gentamicin), and high-dose or multiple NSAIDs [see Warnings and Precautions (5.4)].

7.5 Established and Other Potentially Significant Interactions

Table 5 provides a listing of established or potentially clinically significant drug interactions [see Contraindications (4)]. The drug interactions described are based on studies conducted with either GENVOYA, the components of GENVOYA (elvitegravir, cobicistat, emtricitabine, and tenofovir alafenamide) as individual agents and/or in combination, or are predicted drug interactions that may occur with GENVOYA [for magnitude of interaction, see Clinical Pharmacology (12.3)]. The table includes potentially significant interactions but is not all inclusive.

Table 5 Established and Other Potentially Significant [This table is not all inclusive.] Drug Interactions: Alteration in Dose or Regimen May Be Recommended Based on Drug Interaction Studies or Predicted Interaction
Concomitant Drug Class: Drug Name | Effect on Concentration [↑ = Increase, ↓ = Decrease] | Clinical Comment
Alpha 1-adrenoreceptor antagonist: alfuzosin | ↑ alfuzosin | Coadministration with alfuzosin is contraindicated due to potential for serious and/or life-threatening reactions such as hypotension.
Antiarrhythmics: e.g., amiodarone bepridil digoxin [Indicates that a drug-drug interaction trial was conducted.] disopyramide flecainide systemic lidocaine mexiletine propafenone quinidine | ↑ antiarrhythmics ↑ digoxin | Caution is warranted and therapeutic concentration monitoring, if available, is recommended for antiarrhythmics when coadministered with GENVOYA.
Antibacterials: clarithromycin telithromycin | ↑ clarithromycin ↑ telithromycin ↑ cobicistat | Patients with CLcr greater than or equal to 60 mL/minute: No dosage adjustment of clarithromycin is required. Patients with CLcr between 50 mL/minute and 60 mL/minute: The dosage of clarithromycin should be reduced by 50%.
Anticoagulants: Direct Oral Anticoagulants (DOACs) apixaban rivaroxaban betrixaban dabigatran edoxaban | ↑ apixaban | Due to potentially increased bleeding risk, dosing recommendations for coadministration with GENVOYA depends on the apixaban dose. Refer to apixaban dosing instructions for coadministration with strong CYP3A and P-gp inhibitors in apixaban prescribing information.
Anticoagulants: Direct Oral Anticoagulants (DOACs) apixaban rivaroxaban betrixaban dabigatran edoxaban | ↑ rivaroxaban ↑ betrixaban ↑ dabigatran ↑ edoxaban | Coadministration of rivaroxaban with GENVOYA is not recommended because it may lead to an increased bleeding risk. Due to potentially increased bleeding risk, dosing recommendations for coadministration of betrixaban, dabigatran, or edoxaban with a P-gp inhibitor such as GENVOYA depends on DOAC indication and renal function. Refer to DOAC dosing instructions for coadministration with P-gp inhibitors in DOAC prescribing information.
warfarin | Effect on warfarin unknown | Monitor the international normalized ratio (INR) upon coadministration of warfarin with GENVOYA.
Anticonvulsants: carbamazepine phenobarbital phenytoin | ↓ elvitegravir ↓ cobicistat ↓ TAF | Coadministration with carbamazepine, phenobarbital, or phenytoin is contraindicated due to potential for loss of therapeutic effect and development of resistance.
oxcarbazepine |  | Alternative anticonvulsants should be considered when GENVOYA is administered with oxcarbazepine.
ethosuximide | ↑ ethosuximide | Clinical monitoring is recommended upon coadministration of ethosuximide with GENVOYA.
Antidepressants: Selective Serotonin Reuptake Inhibitors (SSRIs) e.g., paroxetine Tricyclic Antidepressants (TCAs) e.g., amitriptyline desipramine imipramine nortriptyline bupropion trazodone | ↑ SSRIs (except sertraline) ↑ TCAs ↑ trazodone | Careful dosage titration of the antidepressant and monitoring for antidepressant response are recommended when coadministered with GENVOYA.
Antifungals: itraconazole ketoconazole voriconazole | ↑ elvitegravir ↑ cobicistat ↑ itraconazole ↑ ketoconazole ↑ voriconazole | When administering with GENVOYA, the maximum daily dosage of ketoconazole or itraconazole should not exceed 200 mg per day. An assessment of benefit/risk ratio is recommended to justify use of voriconazole with GENVOYA.
Anti-gout: colchicine | ↑ colchicine | GENVOYA is not recommended to be coadministered with colchicine to patients with renal or hepatic impairment. Treatment of gout-flares – coadministration of colchicine in patients receiving GENVOYA: 0.6 mg (1 tablet) × 1 dose, followed by 0.3 mg (half tablet) 1 hour later. Treatment course to be repeated no earlier than 3 days. Prophylaxis of gout-flares – coadministration of colchicine in patients receiving GENVOYA: If the original regimen was 0.6 mg twice a day, the regimen should be adjusted to 0.3 mg once a day. If the original regimen was 0.6 mg once a day, the regimen should be adjusted to 0.3 mg once every other day. Treatment of familial Mediterranean fever – coadministration of colchicine in patients receiving GENVOYA: Maximum daily dosage of 0.6 mg (may be given as 0.3 mg twice a day).
Antimycobacterial: rifampin | ↓ elvitegravir ↓ cobicistat ↓ TAF | Coadministration with rifampin is contraindicated due to potential for loss of therapeutic effect and development of resistance.
rifabutin rifapentine |  | Coadministration of GENVOYA with rifabutin or rifapentine is not recommended.
Antiplatelets:
ticagrelor | ↑ ticagrelor | Coadminstration with ticagrelor is not recommended.
clopidogrel | ↓ clopidogrel active metabolite | Coadministration with clopidogrel is not recommended due to protential reduction of the antiplatelet activity of clopidogrel.
Antipsychotics:
lurasidone | ↑ lurasidone | Coadministration with lurasidone is contraindicated due to potential for serious and/or life-threatening reactions.
pimozide | ↑ pimozide | Coadministration with pimozide is contraindicated due to potential for serious and/or life-threatening reactions such as cardiac arrhythmias.
quetiapine | ↑ quetiapine | Initiation of GENVOYA in patients taking quetiapine: Consider alternative antiretroviral therapy to avoid increases in quetiapine exposure. If coadministration is necessary, reduce the quetiapine dose to 1/6 of the current dose and monitor for quetiapine-associated adverse reactions. Refer to the quetiapine prescribing information for recommendations on adverse reaction monitoring. Initiation of quetiapine in patients taking GENVOYA: Refer to the quetiapine prescribing information for initial dosing and titration of quetiapine.
Other antipsychotics e.g., perphenazine risperidone thioridazine | ↑ antipsychotic | A decrease in dose of the antipsychotics that are metabolized by CYP3A or CYP2D6 may be needed when coadministered with GENVOYA.
Beta-Blockers: e.g., metoprolol timolol | ↑ beta-blockers | Clinical monitoring is recommended and a dosage decrease of the beta blocker may be necessary when these agents are coadministered with GENVOYA.
Calcium Channel Blockers: e.g., amlodipine diltiazem felodipine nicardipine nifedipine verapamil | ↑ calcium channel blockers | Caution is warranted and clinical monitoring is recommended upon coadministration of calcium channel blockers with GENVOYA.
Corticosteroids: e.g., betamethasone budesonide ciclesonide dexamethasone fluticasone methylprednisolone mometasone prednisone triamcinolone | ↓ elvitegravir ↓ cobicistat ↑ corticosteroids | Coadministration with oral dexamethasone or other systemic corticosteroids that induce CYP3A may result in loss of therapeutic effect and development of resistance to elvitegravir. Consider alternative corticosteroids. Coadministration with corticosteroids (all routes of administration) whose exposures are significantly increased by strong CYP3A inhibitors can increase the risk for Cushing's syndrome and adrenal suppression. Alternative corticosteroids including beclomethasone and prednisolone (whose PK and/or PD are less affected by strong CYP3A inhibitors relative to other studied steroids) should be considered, particularly for long-term use.
Endothelin Receptor Antagonists: bosentan | ↑ bosentan | Coadministration of bosentan in patients on GENVOYA: In patients who have been receiving GENVOYA for at least 10 days, start bosentan at 62.5 mg once daily or every other day based upon individual tolerability. Coadministration of GENVOYA in patients on bosentan: Discontinue use of bosentan at least 36 hours prior to initiation of GENVOYA. After at least 10 days following the initiation of GENVOYA, resume bosentan at 62.5 mg once daily or every other day based upon individual tolerability.
Ergot Derivatives: dihydroergotamine ergotamine methylergonovine | ↑ ergot derivatives | Coadministration is contraindicated due to potential for serious and/or life-threatening reactions such as acute ergot toxicity characterized by peripheral vasospasm and ischemia of the extremities and other tissues [see Contraindications (4)].
Herbal Products: St. John's wort (Hypericum perforatum) | ↓ elvitegravir ↓ cobicistat ↓ TAF | Coadministration is contraindicated due to potential for loss of therapeutic effect and development of resistance.
Hormonal Contraceptives: drospirenone/ethinyl estradiol levonorgestrel norgestimate/ethinyl estradiol | ↑ drospirenone ↑ norgestimate ↑ levonorgestrel ↓ ethinyl estradiol | Additional or alternative non-hormonal forms of contraception should be considered when estrogen based contraceptives are coadministered with GENVOYA. Plasma concentrations of drospirenone may be increased when coadministered with cobicistat-containing products. Clinical monitoring is recommended due to the potential for hyperkalemia. The effects of increases in the concentration of the progestational component norgestimate are not fully known and can include increased risk of insulin resistance, dyslipidemia, acne, and venous thrombosis. The potential risks and benefits associated with coadministration of norgestimate/ethinyl estradiol with GENVOYA should be considered, particularly in patients who have risk factors for these events. The effect of GENVOYA on other hormonal contraceptives (e.g., contraceptive patch, contraceptive vaginal ring, or injectable contraceptives) or oral contraceptives containing progestogens other than drospirenone, levonorgestrel, or norgestimate has not been studied; therefore, alternative (non-hormonal) methods of contraception can be considered.
Immuno-suppressants: e.g., cyclosporine (CsA) sirolimus tacrolimus | ↑ immuno-suppressants ↑ elvitegravir (with CsA) ↑ cobicistat (with CsA) | Therapeutic monitoring of the immunosuppressive agents is recommended upon coadministration with GENVOYA. Monitor for adverse events associated with GENVOYA when coadministered with cyclosporine.
Lipid-modifying Agents:
HMG-CoA Reductase Inhibitors: lovastatin simvastatin | ↑ lovastatin ↑ simvastatin | Coadministration with lovastatin or simvastatin is contraindicated due to potential for serious reactions such as myopathy including rhabdomyolysis.
atorvastatin | ↑ atorvastatin | Initiate atorvastatin with the lowest starting dose of atorvastatin and titrate carefully while monitoring for safety (e.g., myopathy). Do not exceed a dosage of atorvastatin 20 mg daily.
Other Lipid-modifying Agents: lomitapide | ↑ lomitapide | Coadministration with lomitapide is contraindicated due to potential for markedly increased transaminases.
Narcotic Analgesics: buprenorphine/ naloxone | ↑ buprenorphine ↑ norbuprenorphine ↓ naloxone | No dosage adjustment of buprenorphine/naloxone is required upon coadministration with GENVOYA. Patients should be closely monitored for sedation and cognitive effects.
fentanyl | ↑ fentanyl | Careful monitoring of therapeutic and adverse effects of fentanyl (including potentially fatal respiratory depression) is recommended with coadministration.
tramadol | ↑ tramadol | A dose decrease may be needed for tramadol with concomitant use.
Inhaled Beta Agonist: salmeterol | ↑ salmeterol | Coadministration of salmeterol and GENVOYA is not recommended. Coadministration of salmeterol with GENVOYA may result in increased risk of cardiovascular adverse events associated with salmeterol, including QT prolongation, palpitations, and sinus tachycardia.
Medications or Oral Supplements Containing Polyvalent Cations (e.g., Mg, Al, Ca, Fe, Zn): calcium or iron supplements, including multivitamins cation-containing antacids or laxatives sucralfate buffered medications | ↓ elvitegravir | Separate GENVOYA and administration of medications, antacids, or oral supplements containing polyvalent cations by at least 2 hours.
Phosphodiesterase-5 (PDE5) Inhibitors: sildenafil tadalafil vardenafil | ↑ PDE5 inhibitors | Use of PDE-5 inhibitors for pulmonary arterial hypertension (PAH): Coadministration of sildenafil with GENVOYA is contraindicated when used for treatment of PAH, due to potential for PDE-5 inhibitor associated adverse reactions, including hypotension, syncope, visual disturbances, and priapism. The following dose adjustments are recommended for the use of tadalafil with GENVOYA: Coadministration of tadalafil in patients on GENVOYA: In patients receiving GENVOYA for at least 1 week, start tadalafil at 20 mg once daily. Increase tadalafil dose to 40 mg once daily based upon individual tolerability. Coadministration of GENVOYA in patients on tadalafil: Avoid use of tadalafil during the initiation of GENVOYA. Stop tadalafil at least 24 hours prior to starting GENVOYA. After at least one week following initiation of GENVOYA, resume tadalafil at 20 mg once daily. Increase tadalafil dose to 40 mg once daily based upon individual tolerability. Use of PDE-5 inhibitors for erectile dysfunction: Sildenafil at a single dose not exceeding 25 mg in 48 hours, vardenafil at a single dose not exceeding 2.5 mg in 72 hours, or tadalafil at a single dose not exceeding 10 mg in 72 hours can be used with increased monitoring for PDE-5 inhibitor associated with adverse events.
Sedative/hypnotic: midazolam (oral) triazolam | ↑ midazolam ↑ triazolam | Coadministration with triazolam or orally administered midazolam is contraindicated due to potential for serious and/or life-threatening reactions such as prolonged or increased sedation or respiratory depression.
Other benzodiazepines: e.g., parenterally administered midazolam clorazepate diazepam estazolam flurazepam | ↑ sedatives/hypnotics | Triazolam and orally administered midazolam are extensively metabolized by CYP3A. Coadministration of triazolam or orally administered midazolam with GENVOYA may cause large increases in the concentrations of these benzodiazepines. Coadministration of parenteral midazolam with GENVOYA should be done in a setting that ensures close clinical monitoring and appropriate medical management in case of respiratory depression and/or prolonged sedation. Dosage reduction for midazolam should be considered, especially if more than a single dose of midazolam is administered.
buspirone zolpidem |  | With other sedative/hypnotics, dose reduction may be necessary and clinical monitoring is recommended.

7.6 Drugs without Clinically Significant Interactions with GENVOYA

Based on drug interaction studies conducted with the components of GENVOYA, no clinically significant drug interactions have been observed or are expected when GENVOYA is combined with the following drugs: famciclovir, famotidine, ledipasvir, methadone, omeprazole, prasugrel (active metabolite), sertraline, sofosbuvir, velpatasvir, and voxilaprevir.

8 USE IN SPECIFIC POPULATIONS

8.1 Pregnancy

Pregnancy Exposure Registry

There is a pregnancy exposure registry that monitors pregnancy outcomes in individuals exposed to GENVOYA during pregnancy. Healthcare providers are encouraged to register patients by calling the Antiretroviral Pregnancy Registry (APR) at 1-800-258-4263.

Risk Summary

GENVOYA is not recommended during pregnancy [see Dosage and Administration (2.5)]. A literature report evaluating the pharmacokinetics of antiretrovirals during pregnancy demonstrated substantially lower exposures of elvitegravir and cobicistat in the second and third trimesters (see Data).

Prospective pregnancy data from the APR are not sufficient to adequately assess the risk of birth defects or miscarriage. However, elvitegravir (EVG), cobicistat (COBI), emtricitabine (FTC), and tenofovir alafenamide (TAF) use during pregnancy have been evaluated in a limited number of individuals as reported to the APR. Available data from the APR show no statistically significant difference in the overall risk of major birth defects for EVG, COBI, FTC or TAF compared with the background rate for major birth defects of 2.7% in a U.S. reference population of the Metropolitan Atlanta Congenital Defects Program (MACDP) (see Data). The rate of miscarriage is not reported in the APR. In the U.S. general population, the estimated background risk of miscarriage in clinically recognized pregnancies is 15-20%.

In animal studies, no adverse developmental effects were observed when the components of GENVOYA were administered separately during the period of organogenesis at exposures up to 23 and 0.2 times (rat and rabbits, respectively: elvitegravir), 1.6 and 3.8 times (rats and rabbits, respectively: cobicistat), 60 and 108 times (mice and rabbits, respectively; emtricitabine) and equal to and 53 times (rats and rabbits, respectively; TAF) the exposure at the recommended daily dosage of these components in GENVOYA (see Data). Likewise, no adverse developmental effects were seen when elvitegravir or cobicistat was administered to rats through lactation at exposures up to 18 times or 1.2 times, respectively, the human exposure at the recommended therapeutic dose, and when emtricitabine was administered to mice through lactation at exposures up to approximately 60 times the exposure at the recommended daily dose. No adverse effects were observed in the offspring when TDF was administered through lactation at tenofovir exposures of approximately 14 times the exposure at the recommended daily dosage of GENVOYA.

Data

Human Data

A prospective study, reported in the literature, enrolled 30 pregnant women living with HIV who were receiving elvitegravir and cobicistat-based regimens in the second or third trimesters of pregnancy and through 6 to 12 weeks postpartum to evaluate the pharmacokinetics (PK) of antiretrovirals during pregnancy. Twenty-eight women completed the study through the postpartum period. Paired pregnancy/postpartum PK data were available from 14 and 24 women for the second and third trimesters, respectively. Exposures of elvitegravir and cobicistat were substantially lower during the second and third trimesters compared to postpartum. The proportion of pregnant women who were virologically suppressed was 77% in the second trimester, 92% in the third trimester, and 76% postpartum. No correlation was observed between viral suppression and elvitegravir exposure. HIV status was also assessed for infants: 25 were uninfected, 2 had indeterminate status, and no information was available for 3 infants.

Prospective reports from the APR of overall major birth defects in pregnancies exposed to the components of GENVOYA are compared with a U.S. background major birth defect rate. Methodological limitations of the APR include the use of MACDP as the external comparator group. Limitations of using an external comparator include differences in methodology and populations, as well as confounding due to the underlying disease.

Elvitegravir (EVG):

Based on prospective reports to the APR of over 440 exposures to EVG-containing regimens during pregnancy resulting in live births (including over 350 exposed in the first trimester and 70 exposed in the second/third trimester), the prevalence of birth defects in live births was 3.0% (95% CI: 1.5% to 5.2%) and 1.4% (95% CI: 0.0% to 7.7%) following first and second/third trimester exposure, respectively, to EVG-containing regimens.

Cobicistat (COBI):

Based on prospective reports to the APR of over 560 exposures to COBI-containing regimens during pregnancy resulting in live births (including over 470 exposed in the first trimester and over 80 exposed in the second/third trimester), the prevalence of birth defects in live births was 3.6% (95% CI: 2.1% to 5.7%) and 1.1% (95% CI: 0.0% to 6.2%) following first and second/third trimester, respectively, to COBI-containing regimens.

Emtricitabine (FTC):

Based on prospective reports to the APR of over 5,400 exposures to FTC-containing regimens during pregnancy resulting in live births (including over 3,900 exposed in the first trimester and over 1,500 exposed in the second/third trimester), the prevalence of birth defects in live births was 2.6% (95% CI: 2.2% to 3.2%) and 2.7% (95% CI: 1.9% to 3.7%) following first and second/third trimester exposure, respectively, to FTC-containing regimens.

Tenofovir Alafenamide (TAF):

Based on prospective reports to the APR of over 660 exposures to TAF-containing regimens during pregnancy resulting in live births (including over 520 exposed in the first trimester and over 130 exposed in the second/third trimester), the prevalence of birth defects in live births was 4.2% (95% CI: 2.6% to 6.3%) and 3.0% (95% CI: 0.8% to 7.5%) following first and second/third trimester exposure, respectively, to TAF-containing regimens.

Animal Data

Elvitegravir:

Elvitegravir was administered orally to pregnant rats (0, 300, 1000, and 2000 mg/kg/day) and rabbits (0, 50, 150, and 450 mg/kg/day) through organogenesis (on gestation days 7 through 17 and days 7 through 19, respectively). No significant toxicological effects were observed in embryo-fetal toxicity studies performed with elvitegravir in rats at exposures (AUC) approximately 23 times and in rabbits at approximately 0.2 times the human exposures at the recommended daily dose. In a pre/postnatal developmental study, elvitegravir was administered orally to rats at doses of 0, 300, 1000, and 2000 mg/kg from gestation day 7 to day 20 of lactation. At doses of 2000 mg/kg/day of elvitegravir, neither maternal nor developmental toxicity was noted. Systemic exposures (AUC) at this dose were 18 times the human exposures at the recommended daily dose.

Cobicistat:

Cobicistat was administered orally to pregnant rats at doses of 0, 25, 50, 125 mg/kg/day on gestation day 6 to 17. Increases in post-implantation loss and decreased fetal weights were observed at a maternal toxic dose of 125 mg/kg/day. No malformations were noted at doses up to 125 mg/kg/day. Systemic exposures (AUC) at 50 mg/kg/day in pregnant females were 1.6 times higher than human exposures at the recommended daily dose.

In pregnant rabbits, cobicistat was administered orally at doses of 0, 20, 50, and 100 mg/kg/day during gestation days 7 to 20. No maternal or embryo/fetal effects were noted at the highest dose of 100 mg/kg/day. Systemic exposures (AUC) at 100 mg/kg/day were 3.8 times higher than human exposures at the recommended daily dose.

In a pre/postnatal developmental study in rats, cobicistat was administered orally at doses of 0, 10, 30, and 75 mg/kg from gestation day 6 to postnatal day 20, 21, or 22. At doses of 75 mg/kg/day of cobicistat, neither maternal nor developmental toxicity was noted. Systemic exposures (AUC) at this dose were 1.2 times the human exposures at the recommended daily dose.

Emtricitabine:

Emtricitabine was administered orally to pregnant mice (250, 500, or 1000 mg/kg/day) and rabbits (100, 300, or 1000 mg/kg/day) through organogenesis (on gestation days 6 through 15, and 7 through 19, respectively). No significant toxicological effects were observed in embryo-fetal toxicity studies performed with emtricitabine in mice at exposures (AUC) approximately 60 times higher and in rabbits at approximately 108 times higher than human exposures at the recommended daily dose.

In a pre/postnatal development study with emtricitabine, mice were administered doses up to 1000 mg/kg/day; no significant adverse effects directly related to drug were observed in the offspring exposed daily from before birth (in utero) through sexual maturity at daily exposures (AUC) of approximately 60 times higher than human exposures at the recommended daily dose.

Tenofovir Alafenamide (TAF):

TAF was administered orally to pregnant rats (25, 100, or 250 mg/kg/day) and rabbits (10, 30, or 100 mg/kg/day) through organogenesis (on gestation days 6 through 17, and 7 through 20, respectively). No adverse embryo-fetal effects were observed in rats and rabbits at TAF exposures similar to (rats) and approximately 53 (rabbits) times higher than the exposure in humans at the recommended daily dose of GENVOYA. TAF is rapidly converted to tenofovir; the observed tenofovir exposure in rats and rabbits were 59 (rats) and 93 (rabbits) times higher than human tenofovir exposures at the recommended daily doses. Since TAF is rapidly converted to tenofovir and lower tenofovir exposures in rats and mice were observed after TAF administration compared to TDF administration, a pre/postnatal development study in rats was conducted only with TDF. Doses up to 600 mg/kg/day were administered through lactation; no adverse effects were observed in the offspring on gestation day 7 [and lactation day 20] at tenofovir exposures of approximately 14 [21] times higher than the exposures in humans at the recommended daily dose of GENVOYA.

8.2 Lactation

Risk Summary

The Centers for Disease Control and Prevention recommend that HIV-infected mothers not breastfeed their infants to avoid risking postnatal transmission of HIV.

Based on published data, emtricitabine has been shown to be present in human breast milk; it is unknown if elvitegravir, cobicistat, and TAF are present in human breast milk. Elvitegravir and cobicistat are present in rat milk, and tenofovir has been shown to be present in the milk of lactating rats and rhesus monkeys after administration of TDF [see Data]. It is unknown if TAF is present in animal milk.

It is not known if GENVOYA affects milk production or has effects on the breastfed child. Because of the potential for 1) HIV transmission (in HIV-negative infants); 2) developing viral resistance (in HIV-positive infants); and 3) adverse reactions in a breastfed infant similar to those seen in adults, instruct mothers not to breastfeed if they are receiving GENVOYA.

Data

Animal Data

Elvitegravir: During the pre/postnatal developmental toxicology study at doses up to 2000 mg/kg/day, a mean elvitegravir milk to plasma ratio of 0.1 was measured 30 minutes after administration to rats on lactation day 14.

Cobicistat: During the pre/postnatal developmental toxicology study at doses up to 75 mg/kg/day, mean cobicistat milk to plasma ratio of up to 1.9 was measured 2 hours after administration to rats on lactation day 10.

Tenofovir Alafenamide: Studies in rats and monkeys have demonstrated that tenofovir is secreted in milk. During the pre/postnatal developmental toxicology study, tenofovir was excreted into the milk of lactating rats following oral administration of TDF (up to 600 mg/kg/day) at up to approximately 24% of the median plasma concentration in the highest dosed animals at lactation day 11. Tenofovir was excreted into the milk of lactating rhesus monkeys, following a single subcutaneous (30 mg/kg) dose of tenofovir, at concentrations up to approximately 4% of plasma concentration resulting in exposure (AUC) of approximately 20% of plasma exposure.

8.4 Pediatric Use

The safety and effectiveness of GENVOYA for the treatment of HIV-1 infection was established in pediatric patients with body weight greater than or equal to 25 kg [see Indications and Usage (1) and Dosage and Administration (2.2)].

Use of GENVOYA in pediatric patients less than 18 years of age and weighing at least 25 kg is supported by studies in adults and by an open-label study in antiretroviral treatment-naïve HIV-1 infected pediatric subjects aged 12 to less than 18 years and weighing at least 35 kg (cohort 1 of Study 106, N=50) and in virologically-suppressed pediatric subjects aged 6 to less than 12 years and weighing at least 25 kg (cohort 2 of Study 106, N=52). The safety and efficacy of GENVOYA in adolescent subjects was similar to that in adults [see Adverse Reactions (6.1), Clinical Pharmacology (12.3), and Clinical Studies (14.5)].

The safety and efficacy of GENVOYA in subjects 6 to 12 years of age weighing at least 25 kg was similar to that in antiretroviral treatment-naïve adults and adolescents with the exception of a decrease from baseline CD4+ cell count [see Adverse Reactions (6.1), Clinical Pharmacology (12.3), and Clinical Studies (14.5)].

A pharmacokinetic evaluation of a reduced strength GENVOYA formulation containing 90 mg of EVG, 90 mg of COBI, 120 mg of FTC, and 6 mg TAF was performed in 27 virologically-suppressed pediatric patients at least 2 years of age and weighing at least 14 to less than 25 kg (cohort 3 of Study 106). Virologic, immunologic, and safety outcomes were similar to those observed in cohort 2 of Study 106. No clinically meaningful differences in drug exposures except EVG were identified between pediatric patients in cohort 3 receiving the reduced strength formulation and adults receiving the GENVOYA tablet containing 150 mg of EVG,150 mg of COBI, 200 mg of FTC, and 10 mg TAF. The median observed EVG Ctrough values in subjects in cohort 3 were significantly lower than the values correlated with efficacy in adults. Therefore, efficacy cannot be extrapolated from adults to pediatric patients weighing 14 to 25 kg.

Safety and effectiveness of GENVOYA in pediatric patients weighing less than 25 kg have not been established.

8.5 Geriatric Use

Clinical trials of GENVOYA included 97 subjects (80 receiving GENVOYA) aged 65 years and over. No differences in safety or efficacy have been observed between elderly subjects and adults between 18 and less than 65 years of age.

8.6 Renal Impairment

The pharmacokinetics, safety, and virologic and immunologic responses of GENVOYA in HIV-1 infected adult subjects with renal impairment (estimated creatinine clearance between 30 and 69 mL per minute by Cockcroft-Gault method) were evaluated in 248 subjects in an open-label trial, Study 112.

The pharmacokinetics, safety, virologic and immunologic responses of GENVOYA in HIV-1 infected adult subjects with ESRD (estimated creatinine clearance of less than 15 mL per minute by Cockcroft-Gault method) receiving chronic hemodialysis were evaluated in 55 subjects in an open-label trial, Study 1825 [see Adverse Reactions (6.1) and Clinical Studies (14.4)].

No dosage adjustment of GENVOYA is recommended in patients with estimated creatinine clearance greater than or equal to 30 mL per minute, or in adult patients with ESRD (estimated creatinine clearance below 15 mL per minute) who are receiving chronic hemodialysis. On days of hemodialysis, administer GENVOYA after completion of hemodialysis treatment [see Dosage and Administration (2.2)].

GENVOYA is not recommended in patients with severe renal impairment (estimated creatinine clearance of 15 to below 30 mL per minute), or in patients with ESRD who are not receiving chronic hemodialysis, as the safety of GENVOYA has not been established in these populations [see Dosage and Administration (2.3), Warnings and Precautions (5.4) and Clinical Pharmacology (12.3)].

8.7 Hepatic Impairment

No dosage adjustment of GENVOYA is required in patients with mild (Child-Pugh Class A) or moderate (Child-Pugh Class B) hepatic impairment. GENVOYA has not been studied in patients with severe hepatic impairment (Child-Pugh Class C). Therefore, GENVOYA is not recommended for use in patients with severe hepatic impairment [see Dosage and Administration (2.4) and Clinical Pharmacology (12.3)].

10 OVERDOSAGE

No data are available on overdose of GENVOYA in patients. If overdose occurs, monitor the patient for evidence of toxicity. Treatment of overdose with GENVOYA consists of general supportive measures including monitoring of vital signs as well as observation of the clinical status of the patient.

Elvitegravir: Limited clinical experience is available at doses higher than the recommended dose of elvitegravir in GENVOYA. In one study, elvitegravir (administered with the CYP3A inhibitor cobicistat) equivalent to 2 times the therapeutic dose of 150 mg once daily for 10 days was administered to 42 healthy subjects. No severe adverse reactions were reported. The effects of higher doses are not known. As elvitegravir is highly bound to plasma proteins, it is unlikely that it will be significantly removed by hemodialysis or peritoneal dialysis.

Cobicistat: Limited clinical experience is available at doses higher than the recommended dose of cobicistat in GENVOYA. In two studies, a single dose of cobicistat 400 mg (2.7 times the dose in GENVOYA) was administered to a total of 60 healthy subjects. No severe adverse reactions were reported. The effects of higher doses are not known. As cobicistat is highly bound to plasma proteins, it is unlikely that it will be significantly removed by hemodialysis or peritoneal dialysis.

Emtricitabine: Limited clinical experience is available at doses higher than the recommended dose of emtricitabine in GENVOYA. In one clinical pharmacology study, single doses of emtricitabine 1200 mg (6 times the dose in GENVOYA) were administered to 11 subjects. No severe adverse reactions were reported. The effects of higher doses are not known.

Hemodialysis treatment removes approximately 30% of the emtricitabine dose over a 3-hour dialysis period starting within 1.5 hours of emtricitabine dosing (blood flow rate of 400 mL per minute and a dialysate flow rate of 600 mL per minute). It is not known whether emtricitabine can be removed by peritoneal dialysis.

Tenofovir alafenamide (TAF): Limited clinical experience is available at doses higher than the recommended dose of TAF in GENVOYA. A single dose of 125 mg TAF (12.5 times the dose in GENVOYA) was administered to 48 healthy subjects; no serious adverse reactions were reported. The effects of higher doses are unknown. Tenofovir is efficiently removed by hemodialysis with an extraction coefficient of approximately 54%.

11 DESCRIPTION

GENVOYA (elvitegravir, cobicistat, emtricitabine, and tenofovir alafenamide) is a fixed-dose combination tablet containing elvitegravir (EVG), cobicistat (COBI), emtricitabine (FTC), and tenofovir alafenamide (TAF) for oral administration.

- EVG is an HIV-1 integrase strand transfer inhibitor.
- COBI is a mechanism-based inhibitor of cytochrome P450 (CYP) enzymes of the CYP3A family.
- FTC, a synthetic nucleoside analog of cytidine, is an HIV nucleoside analog reverse transcriptase inhibitor (HIV NRTI).
- TAF, an HIV NRTI, is converted in vivo to tenofovir, an acyclic nucleoside phosphonate (nucleotide) analog of adenosine 5'-monophosphate.

Each tablet contains 150 mg of EVG, 150 mg of COBI, 200 mg of FTC, and 10 mg of TAF (equivalent to 11.2 mg of tenofovir alafenamide fumarate). The tablets include the following inactive ingredients: croscarmellose sodium, hydroxypropyl cellulose, lactose monohydrate, magnesium stearate, microcrystalline cellulose, silicon dioxide, and sodium lauryl sulfate. The tablets are film-coated with a coating material containing FD&C Blue No. 2/indigo carmine aluminum lake, iron oxide yellow, polyethylene glycol, polyvinyl alcohol, talc, and titanium dioxide.

Elvitegravir: The chemical name of elvitegravir is 6-(3-chloro-2-fluorobenzyl)-1-[(2S)-1-hydroxy-3-methylbutan-2-yl]-7-methoxy-4-oxo-1,4-dihydroquinoline-3-carboxylic acid.

It has a molecular formula of C23H23ClFNO5 and a molecular weight of 447.88. It has the following structural formula:

Elvitegravir is a white to pale yellow powder with a solubility of less than 0.3 micrograms per mL in water at 20 °C.

Cobicistat: The chemical name for cobicistat is 2,7,10,12-tetraazatridecanoic acid, 12-methyl-13-[2-(1-methylethyl)-4-thiazolyl]-9-[2-(4-morpholinyl)ethyl]-8,11-dioxo-3,6-bis(phenylmethyl)-, 5-thiazolylmethyl ester, (3R,6R,9S)-.

It has a molecular formula of C40H53N7O5S2 and a molecular weight of 776.02. It has the following structural formula:

Cobicistat is adsorbed onto silicon dioxide. Cobicistat on silicon dioxide drug substance is a white to pale yellow powder with a solubility of 0.1 mg per mL in water at 20 °C.

Emtricitabine: The chemical name of emtricitabine is 4-amino-5-fluoro-1-(2R-hydroxymethyl-1,3-oxathiolan-5S-yl)-(1H)-pyrimidin-2-one. Emtricitabine is the (-)-enantiomer of a thio analog of cytidine, which differs from other cytidine analogs in that it has a fluorine in the 5 position.

It has a molecular formula of C8H10FN3O3S and a molecular weight of 247.24. It has the following structural formula:

Emtricitabine is a white to off-white powder with a solubility of approximately 112 mg per mL in water at 25 °C.

Tenofovir alafenamide (TAF): The chemical name of tenofovir alafenamide fumarate drug substance is L-alanine, N-[(S)-[[(1R)-2-(6-amino-9H-purin-9-yl)-1-methylethoxy]methyl]phenoxyphosphinyl]-, 1-methylethyl ester, (2E)-2-butenedioate (2:1).

It has an empirical formula of C21H29O5N6P∙½(C4H4O4) and a formula weight of 534.5. It has the following structural formula:

Tenofovir alafenamide fumarate is a white to off-white or tan powder with a solubility of 4.7 mg per mL in water at 20 °C.

12 CLINICAL PHARMACOLOGY

12.1 Mechanism of Action

GENVOYA is a fixed-dose combination of antiretroviral drugs elvitegravir (plus the CYP3A inhibitor cobicistat), emtricitabine, and tenofovir alafenamide [see Microbiology (12.4)].

12.2 Pharmacodynamics

Cardiac Electrophysiology

Thorough QT studies have been conducted for elvitegravir, cobicistat, and TAF. The effect of emtricitabine or the combination regimen GENVOYA on the QT interval is not known.

Elvitegravir: In a thorough QT/QTc study in 126 healthy subjects, elvitegravir (coadministered with 100 mg ritonavir) 125 mg and 250 mg (0.83 and 1.67 times the dose in GENVOYA) did not affect the QT/QTc interval and did not prolong the PR interval.

Cobicistat: In a thorough QT/QTc study in 48 healthy subjects, a single dose of cobicistat 250 mg and 400 mg (1.67 and 2.67 times the dose in GENVOYA) did not affect the QT/QTc interval. Prolongation of the PR interval was noted in subjects receiving cobicistat. The maximum mean (95% upper confidence bound) difference in PR from placebo after baseline-correction was 9.5 (12.1) msec for the 250 mg cobicistat dose and 20.2 (22.8) for the 400 mg cobicistat dose. Because the 150 mg cobicistat dose used in the GENVOYA fixed-dose combination tablet is lower than the lowest dose studied in the thorough QT study, it is unlikely that treatment with GENVOYA will result in clinically relevant PR prolongation.

Tenofovir Alafenamide (TAF): In a thorough QT/QTc study in 48 healthy subjects, TAF at the therapeutic dose or at a supratherapeutic dose approximately 5 times the recommended therapeutic dose did not affect the QT/QTc interval and did not prolong the PR interval.

Effects on Serum Creatinine

The effect of cobicistat on serum creatinine was investigated in a Phase 1 study in subjects with an estimated creatinine clearance of at least 80 mL per minute (N=18) and with an estimated creatinine clearance of 50 to 79 mL per minute (N=12). A statistically significant change of estimated creatinine clearance from baseline was observed after 7 days of treatment with cobicistat 150 mg among subjects with an estimated creatinine clearance of at least 80 mL per minute (−9.9 ± 13.1 mL/min) and subjects with an estimated creatinine clearance between 50 and 79 mL per minute (−11.9 ± 7.0 mL per minute). These decreases in estimated creatinine clearance were reversible after cobicistat was discontinued. The actual glomerular filtration rate, as determined by the clearance of probe drug iohexol, was not altered from baseline following treatment of cobicistat among subjects with an estimated creatinine clearance of at least 50 mL per minute, indicating cobicistat inhibits tubular secretion of creatinine, reflected as a reduction in estimated creatinine clearance without affecting the actual glomerular filtration rate.

12.3 Pharmacokinetics

Absorption, Distribution, Metabolism, and Excretion

The pharmacokinetic (PK) properties of the components of GENVOYA are provided in Table 6. The multiple dose PK parameters of elvitegravir, cobicistat, emtricitabine, TAF and its metabolite tenofovir are provided in Table 7.

Table 6 Pharmacokinetic Properties of the Components of GENVOYA
 | Elvitegravir | Cobicistat | Emtricitabine | TAF
Absorption
Tmax (h) | 4 | 3 | 3 | 1
Effect of light meal (relative to fasting): AUC Ratio [Values refer to geometric mean ratio in AUC [fed / fasted] and (90% confidence interval). Elvitegravir light meal=~373 kcal, 20% fat; GENVOYA light meal=~400 kcal, 20% fat; elvitegravir and GENVOYA high fat meal=~800 kcal, 50% fat. Based on the effect of food on elvitegravir, GENVOYA should be taken with food.] | 1.34 (1.19, 1.51) | 1.03 (0.90, 1.17) | 0.95 (0.91, 1.00) | 1.15 (1.07, 1.24)
Effect of high fat meal (relative to fasting): AUC Ratio | 1.87 (1.66, 2.10) | 0.83 (0.73, 0.95) | 0.96 (0.92, 1.00) | 1.18 (1.09, 1.26)
Distribution
% Bound to human plasma proteins | ~99 | ~98 | <4 | ~80
Source of protein binding data | Ex vivo | In vitro | In vitro | Ex vivo
Blood-to-plasma ratio | 0.73 | 0.5 | 0.6 | 1.0
Metabolism
Metabolism | CYP3A (major) UGT1A1/3 (minor) | CYP3A (major) CYP2D6 (minor) | Not significantly metabolized | Cathepsin A [In vivo, TAF is hydrolyzed within cells to form tenofovir (major metabolite), which is phosphorylated to the active metabolite, tenofovir diphosphate. In vitro studies have shown that TAF is metabolized to tenofovir by cathepsin A in PBMCs and macrophages; and by CES1 in hepatocytes. Upon coadministration with the moderate CYP3A inducer probe efavirenz, TAF exposure was not significantly affected.] (PBMCs) CES1 (hepatocytes) CYP3A (minimal)
Elimination
Major route of elimination | Metabolism | Metabolism | Glomerular filtration and active tubular secretion | Metabolism (>80% of oral dose)
t1/2 (h) [t1/2 values refer to median terminal plasma half-life. Note that the pharmacologically active metabolite, tenofovir diphosphate, has a half-life of 150–180 hours within PBMCs.] | 12.9 | 3.5 | 10 | 0.51
% Of dose excreted in urine [Dosing in mass balance studies: elvitegravir (single dose administration of [^14C] elvitegravir coadministered with 100 mg ritonavir); cobicistat (single dose administration of [^14C] cobicistat after multiple dosing of cobicistat for six days); emtricitabine (single dose administration of [^14C] emtricitabine after multiple dosing of emtricitabine for ten days); TAF (single dose administration of [^14C] TAF).] | 6.7 | 8.2 | 70 | <1%
% Of dose excreted in feces | 94.8 | 86.2 | 13.7 | 31.7
PBMCs = peripheral blood mononuclear cells; CES1 = carboxylesterase 1.

Table 7 Multiple Dose Pharmacokinetic Parameters of Elvitegravir, Cobicistat, Emtricitabine, Tenofovir Alafenamide (TAF) and its Metabolite Tenofovir Following Oral Administration of GENVOYA with Food in HIV-Infected Adults
Parameter Mean (CV%) | Elvitegravir [From Intensive PK analysis in a Phase 2 trial in HIV infected adults, Study 102 (N=19).] | Cobicistat | Emtricitabine | TAF [From Population PK analysis in two trials of treatment-naïve adults with HIV-1 infection, Studies 104 and 111 (N=539).] | Tenofovir [From Population PK analysis in two trials of treatment-naïve adults with HIV-1 infection, Studies 104 and 111 (N=841).]
Cmax (microgram per mL) | 2.1 (33.7) | 1.5 (28.4) | 2.1 (20.2) | 0.16 (51.1) | 0.02 (26.1)
AUCtau (microgram∙hour per mL) | 22.8 (34.7) | 9.5 (33.9) | 11.7 (16.6) | 0.21 (71.8) | 0.29 (27.4)
Ctrough (microgram per mL) | 0.29 (61.7) | 0.02 (85.2) | 0.10 (46.7) | NA | 0.01 (28.5)
CV = Coefficient of Variation; NA = Not Applicable

Special Populations

Geriatric Patients

Pharmacokinetics of elvitegravir, cobicistat, emtricitabine and tenofovir have not been fully evaluated in the elderly (65 years of age and older). Age does not have a clinically relevant effect on exposures of TAF up to 75 years of age [see Use in Specific Populations (8.5)].

Pediatric Patients

Mean exposures of elvitegravir, cobicistat, and TAF achieved in 24 pediatric subjects aged 12 to less than 18 years who received thedose of GENVOYA containing 150 mg EVG, 150 mg COBI, 200 mg FTC, and 10 mg TAF in Study 106 were decreased compared to exposures achieved in treatment-naïve adults receiving the same dose of GENVOYA, but were overall deemed acceptable based on exposure-response relationships; emtricitabine exposure in adolescents was similar to that in treatment-naïve adults (Table 8).

Table 8 Multiple Dose Pharmacokinetic Parameters of Elvitegravir, Cobicistat, Emtricitabine, Tenofovir Alafenamide (TAF) and its Metabolite Tenofovir Following Oral Administration of GENVOYA in HIV-Infected Pediatric Subjects Aged 12 to less than 18 Years [From Intensive PK analysis in a trial in treatment-naïve pediatric subjects with HIV-1 infection, cohort 1 of Study 106 (N=24).]
Parameter Mean (CV%) | Elvitegravir | Cobicistat | Emtricitabine | TAF | Tenofovir
Cmax (microgram per mL) | 2.2 (19.2) | 1.2 (35.0) | 2.3 (22.5) | 0.17 (64.4) | 0.02 (23.7)
AUCtau (microgram∙hour per mL) | 23.8 (25.5) | 8.2 [N=23] (36.1) | 14.4 (23.9) | 0.20 (50.0) | 0.29 (18.8)
Ctrough (microgram per mL) | 0.30 (81.0) | 0.03 [N=15] (180.0) | 0.10 (38.9) | NA | 0.01 (21.4)
CV = Coefficient of Variation; NA = Not Applicable

Exposures of the components of GENVOYA achieved in 23 pediatric subjects between the ages of 6 to less than 12 years who received the dose of GENVOYA containing 150 mg EVG, 150 mg COBI, 200 mg FTC, and 10 mg TAF in Study 106 were higher (20 to 80% for AUC) than exposures achieved in adults receiving the same dose of GENVOYA; the increase was not considered clinically significant as the safety profiles were similar in adult and pediatric patients (Table 9) [see Use in Specific Populations (8.4)].

Table 9 Multiple Dose Pharmacokinetic Parameters of Elvitegravir, Cobicistat, Emtricitabine, Tenofovir Alafenamide (TAF) and its Metabolite Tenofovir Following Oral Administration of GENVOYA in HIV-Infected Pediatric Subjects Aged 6 to less than 12 Years [From Intensive PK analysis in a trial in virologically-suppressed pediatric subjects with HIV-1 infection, cohort 2 of Study 106 (N=23).]
Parameter Mean (CV%) | Elvitegravir | Cobicistat | Emtricitabine | TAF | Tenofovir
Cmax (microgram per mL) | 3.1 (38.7) | 2.1 (46.7) | 3.4 (27.0) | 0.31 (61.2) | 0.03 (20.8)
AUCtau (microgram∙hour per mL) | 33.8 [N=22] (57.8) | 15.9 [N=20] (51.7) | 20.6 (18.9) | 0.33 (44.8) | 0.44 (20.9)
Ctrough (microgram per mL) | 0.37 (118.5) | 0.1 (168.7) | 0.11 (24.1) | NA | 0.02 (24.9)
CV = Coefficient of Variation; NA = Not Applicable

Race, Gender

No clinically significant differences in pharmacokinetics of GENVOYA have been identified based on race or gender.

Patients with Renal Impairment

The pharmacokinetics of GENVOYA in HIV-1 infected subjects with mild or moderate renal impairment (estimated creatinine clearance between 30 and 69 mL per minute by Cockcroft-Gault method), and in HIV-1 infected subjects with ESRD (estimated creatinine clearance of less than 15 mL per minute by Cockcroft-Gault method) receiving chronic hemodialysis were evaluated in subsets of virologically suppressed subjects in respective open-label trials, Study 112 and Study 1825. The pharmacokinetics of elvitegravir, cobicistat, and tenofovir alafenamide were similar among healthy subjects, subjects with mild or moderate renal impairment, and subjects with ESRD receiving chronic hemodialysis; increases in emtricitabine and tenofovir exposures in subjects with renal impairment were not considered clinically relevant (Table 10).

Table 10 Pharmacokinetics of GENVOYA in HIV-Infected Adults with Renal Impairment as Compared to Subjects with Normal Renal Function
 | AUCtau (microgram∙hour per mL) Mean (CV%)
Estimated Creatinine Clearance [By Cockcroft-Gault method.] | ≥90 mL per minute (N=18) [From a Phase 2 study in HIV-infected adults with normal renal function.] | 60–89 mL per minute (N=11) [These subjects from Study 112 had an estimated creatinine clearance between 60 and 69 mL per minute.] | 30–59 mL per minute (N=18) [Study 112.] | <15 mL per minute (N=12) [Study 1825; PK assessed prior to hemodialysis following 3 consecutive daily doses of GENVOYA.]
Emtricitabine | 11.4 (11.9) | 17.6 (18.2) | 23.0 (23.6) | 62.9 (48.0) [N=11.]
Tenofovir | 0.32 (14.9) | 0.46 (31.5) | 0.61 (28.4) | 8.72 (39.4) [N=10.]

Patients with Hepatic Impairment

Elvitegravir and Cobicistat: A study of the pharmacokinetics of elvitegravir (administered with the CYP3A inhibitor cobicistat) was performed in healthy subjects and subjects with moderate hepatic impairment (Child-Pugh Class B). No clinically relevant differences in elvitegravir or cobicistat pharmacokinetics were observed between subjects with moderate hepatic impairment and healthy subjects [see Use in Specific Populations (8.7)].

Emtricitabine: The pharmacokinetics of emtricitabine has not been studied in subjects with hepatic impairment; however, emtricitabine is not significantly metabolized by liver enzymes, so the impact of liver impairment should be limited.

Tenofovir Alafenamide (TAF): Clinically relevant changes in TAF and tenofovir pharmacokinetics were not observed in subjects with mild to moderate (Child-Pugh Class A and B) hepatic impairment [see Use in Specific Populations (8.7)].

Hepatitis B and/or Hepatitis C Virus Co-infection

Elvitegravir: Limited data from population pharmacokinetic analysis (N=24) indicated that hepatitis B and/or C virus infection had no clinically relevant effect on the exposure of elvitegravir (administered with the CYP3A inhibitor cobicistat).

Cobicistat: There were insufficient pharmacokinetic data in the clinical trials to determine the effect of hepatitis B and/or C virus infection on the pharmacokinetics of cobicistat.

Emtricitabine and Tenofovir Alafenamide (TAF): Pharmacokinetics of emtricitabine and TAF have not been fully evaluated in subjects coinfected with hepatitis B and/or C virus.

Drug Interaction Studies

[see also Contraindications (4) and Drug Interactions (7)]

The drug-drug interaction studies described in Tables 11–14 were conducted with GENVOYA, elvitegravir (coadministered with cobicistat or ritonavir), cobicistat administered alone, or TAF (administered alone or coadministered with emtricitabine).

As GENVOYA should not be administered with other antiretroviral medications, information regarding drug-drug interactions with other antiretrovirals agents is not provided.

The effects of coadministered drugs on the exposure of elvitegravir, emtricitabine, and TAF are shown in Table 11, Table 12, and Table 13 respectively. The effects of GENVOYA or its components on the exposure of coadministered drugs are shown in Table 14. For information regarding clinical recommendations, see Drug Interactions (7).

Table 11 Drug Interactions: Changes in Pharmacokinetic Parameters for Elvitegravir in the Presence of the Coadministered Drug [All interaction studies conducted in healthy volunteers.]
Coadministered Drug | Dose of Coadministered Drug (mg) | Elvitegravir Dose (mg) | CYP3A Inhibitor Cobicistat or Ritonavir Dose (mg) | N | Mean Ratio of Elvitegravir Pharmacokinetic Parameters (90% CI); No effect = 1.00
Coadministered Drug | Dose of Coadministered Drug (mg) | Elvitegravir Dose (mg) | CYP3A Inhibitor Cobicistat or Ritonavir Dose (mg) | N | Cmax | AUC | Cmin
Maximum strength antacid [Maximum strength antacid contained 80 mg aluminum hydroxide, 80 mg magnesium hydroxide, and 8 mg simethicone, per mL.] | 20 mL single dose given 4 hours before elvitegravir | 50 single dose | Ritonavir 100 single dose | 8 | 0.95 (0.84,1.07) | 0.96 (0.88,1.04) | 1.04 (0.93,1.17)
Maximum strength antacid [Maximum strength antacid contained 80 mg aluminum hydroxide, 80 mg magnesium hydroxide, and 8 mg simethicone, per mL.] | 20 mL single dose given 4 hours after elvitegravir | 50 single dose | Ritonavir 100 single dose | 10 | 0.98 (0.88,1.10) | 0.98 (0.91,1.06) | 1.00 (0.90,1.11)
Maximum strength antacid [Maximum strength antacid contained 80 mg aluminum hydroxide, 80 mg magnesium hydroxide, and 8 mg simethicone, per mL.] | 20 mL single dose given 2 hours before elvitegravir | 50 single dose | Ritonavir 100 single dose | 11 | 0.82 (0.74,0.91) | 0.85 (0.79,0.91) | 0.90 (0.82,0.99)
Maximum strength antacid [Maximum strength antacid contained 80 mg aluminum hydroxide, 80 mg magnesium hydroxide, and 8 mg simethicone, per mL.] | 20 mL single dose given 2 hours after elvitegravir | 50 single dose | Ritonavir 100 single dose | 10 | 0.79 (0.71,0.88) | 0.80 (0.75,0.86) | 0.80 (0.73,0.89)
Atorvastatin | 10 single dose | 150 once daily [Study conducted with GENVOYA.] | Cobicistat 150 once daily | 16 | 0.91 (0.85,0.98) | 0.92 (0.87,0.98) | 0.88 (0.81,0.96)
Carbamazepine | 200 twice daily | 150 once daily | Cobicistat 150 once daily | 12 | 0.55 (0.49,0.61) | 0.31 (0.28,0.33) | 0.03 (0.02,0.40)
Famotidine | 40 once daily given 12 hours after elvitegravir | 150 once daily | Cobicistat 150 once daily | 10 | 1.02 (0.89,1.17) | 1.03 (0.95,1.13) | 1.18 (1.05,1.32)
Famotidine | 40 once daily given simultaneously with elvitegravir | 150 once daily | Cobicistat 150 once daily | 16 | 1.00 (0.92,1.10) | 1.03 (0.98,1.08) | 1.07 (0.98,1.17)
Ketoconazole | 200 twice daily | 150 once daily | Ritonavir 100 once daily | 18 | 1.17 (1.04,1.33) | 1.48 (1.36,1.62) | 1.67 (1.48,1.88)
Ledipasvir/ Sofosbuvir | 90/400 once daily | 150 once daily | Cobicistat 150 once daily | 30 | 0.98 (0.90,1.07) | 1.11 (1.02,1.20) | 1.46 (1.28,1.66)
Omeprazole | 40 once daily given 2 hours before elvitegravir | 50 once daily | Ritonavir 100 once daily | 9 | 0.93 (0.83,1.04) | 0.99 (0.91,1.07) | 0.94 (0.85,1.04)
Omeprazole | 20 once daily given 2 hours before elvitegravir | 150 once daily | Cobicistat 150 once daily | 11 | 1.16 (1.04,1.30) | 1.10 (1.02,1.19) | 1.13 (0.96,1.34)
Omeprazole | 20 once daily given 12 hours after elvitegravir | 150 once daily | Cobicistat 150 once daily | 11 | 1.03 (0.92,1.15) | 1.05 (0.93,1.18) | 1.10 (0.92,1.32)
Rifabutin | 150 once every other day | 150 once daily | Cobicistat 150 once daily | 12 | 0.91 (0.84,0.99) | 0.79 (0.74,0.85) | 0.33 (0.27,0.40)
Rosuvastatin | 10 single dose | 150 once daily | Cobicistat 150 once daily | 10 | 0.94 (0.83,1.07) | 1.02 (0.91,1.14) | 0.98 (0.83,1.16)
Sertraline | 50 single dose | 150 once daily | Cobicistat 150 once daily | 19 | 0.88 (0.82,0.93) | 0.94 (0.89,0.98) | 0.99 (0.93,1.05)
Sofosbuvir/ Velpatasvir | 400/100 once daily | 150 once daily | Cobicistat 150 once daily | 24 | 0.87 (0.80,0.94) | 0.94 (0.88,1.00) | 1.08 (0.97,1.20)
Sofosbuvir/ Velpatasvir/ Voxilaprevir | 400/100/100 + 100 Voxilaprevir [Study conducted with additional voxilaprevir 100 mg to achieve voxilaprevir exposures expected in HCV-infected patients.] once daily | 150 once daily | Cobicistat 150 once daily | 29 | 0.79 (0.75,0.85) | 0.94 (0.88,1.00) | 1.32 (1.17,1.49)

Table 12 Drug Interactions: Changes in Pharmacokinetic Parameters for Emtricitabine in the Presence of the Coadministered Drug [All interaction studies conducted in healthy volunteers.]
Coadministered Drug | Dose of Coadministered Drug (mg) | Emtricitabine Dose (mg) | N | Mean Ratio of Emtricitabine Pharmacokinetic Parameters (90% CI); No effect = 1.00
Coadministered Drug | Dose of Coadministered Drug (mg) | Emtricitabine Dose (mg) | N | Cmax | AUC | Cmin
Famciclovir | 500 single dose | 200 single dose | 12 | 0.90 (0.80,1.01) | 0.93 (0.87,0.99) | NC

Table 13 Drug Interactions: Changes in Pharmacokinetic Parameters for Tenofovir Alafenamide (TAF) in the Presence of the Coadministered Drug [All interaction studies conducted in healthy volunteers.]
Coadministered Drug | Dose of Coadministered Drug (mg) | TAF Dose (mg) | N | Mean Ratio of TAF Pharmacokinetic Parameters (90% CI); No effect = 1.00
Coadministered Drug | Dose of Coadministered Drug (mg) | TAF Dose (mg) | N | Cmax | AUC | Cmin
Cobicistat | 150 once daily | 8 once daily | 12 | 2.83 (2.20,3.65) | 2.65 (2.29,3.07) | NC
Ledipasvir/ Sofosbuvir | 90/400 once daily | 10 once daily [Study conducted with GENVOYA.] | 30 | 0.90 (0.73,1.11) | 0.86 (0.78,0.95) | NC
Sertraline | 50 single dose | 10 once daily | 19 | 1.00 (0.86,1.16) | 0.96 (0.89,1.03) | NC
Sofosbuvir/ Velpatasvir | 400/100 once daily | 10 once daily | 24 | 0.80 (0.68,0.94) | 0.87 (0.81,0.94) | NC
Sofosbuvir/ Velpatasvir/ Voxilaprevir | 400/100/100 + 100 Voxilaprevir [Study conducted with additional voxilaprevir 100 mg to achieve voxilaprevir exposures expected in HCV-infected patients.] once daily | 10 once daily | 29 | 0.79 (0.68,0.92) | 0.93 (0.85,1.01) | NC
NC = Not Calculated

Table 14 Drug Interactions: Changes in Pharmacokinetic Parameters for Coadministered Drug in the Presence of GENVOYA or the Individual Components [All interaction studies conducted in healthy volunteers.]
Coadministered Drug | Dose of Coadministered Drug (mg) | Elvitegravir Dose (mg) | CYP3A Inhibitor Cobicistat Dose (mg) | FTC Dose (mg) | TAF Dose (mg) | N | Mean Ratio of Coadministered Drug Pharmacokinetic Parameters (90% CI); No effect = 1.00
Coadministered Drug | Dose of Coadministered Drug (mg) | Elvitegravir Dose (mg) | CYP3A Inhibitor Cobicistat Dose (mg) | FTC Dose (mg) | TAF Dose (mg) | N | Cmax | AUC | Cmin
Atorvastatin | 10 single dose | 150 once daily [Study conducted with GENVOYA.] | 150 once daily | 200 once daily | 10 once daily | 16 | 2.32 (1.91,2.82) | 2.60 (2.31,2.93) | NC
Buprenorphine | 16 – 24 once daily | 150 once daily | 150 once daily | N/A | N/A | 17 | 1.12 (0.98,1.27) | 1.35 (1.18,1.55) | 1.66 (1.43,1.93)
Norbuprenorphine | 16 – 24 once daily | 150 once daily | 150 once daily |  |  | 17 | 1.24 (1.03,1.49) | 1.42 (1.22,1.67) | 1.57 (1.31,1.88)
Carbamazepine | 200 twice daily | 150 once daily | 150 once daily | N/A | N/A | 12 | 1.40 (1.32,1.49) | 1.43 (1.36,1.52) | 1.51 (1.41,1.62)
Carbamazepine-10,11-epoxide | 200 twice daily | 150 once daily | 150 once daily |  |  | 12 | 0.73 (0.70,0.78) | 0.65 (0.63,0.66) | 0.59 (0.57,0.61)
Desipramine | 50 single dose | N/A | 150 once daily | N/A | N/A | 8 | 1.24 (1.08,1.44) | 1.65 (1.36,2.02) | NC
Digoxin | 0.5 single dose | N/A | 150 once daily | N/A | N/A | 22 | 1.41 (1.29,1.55) | 1.08 (1.00,1.17) | NC
Famciclovir | 500 single dose | N/A | N/A | 200 single dose | N/A | 12 | 0.93 (0.78,1.11) | 0.91 (0.84,0.99) | N/A
Ledipasvir | 90 once daily | 150 once daily | 150 once daily | 200 once daily | 10 once daily | 30 | 1.65 (1.53,1.78) | 1.79 (1.64,1.96) | 1.93 (1.74,2.15)
Sofosbuvir | 400 once daily | 150 once daily | 150 once daily | 200 once daily | 10 once daily | 30 | 1.28 (1.13,1.47) | 1.47 (1.35,1.59) | N/A
GS-331007 [The predominant circulating inactive metabolite of sofosbuvir.] | 400 once daily | 150 once daily | 150 once daily | 200 once daily | 10 once daily | 30 | 1.29 (1.24,1.35) | 1.48 (1.44,1.53) | 1.66 (1.60,1.73)
Naloxone | 4–6 once daily | 150 once daily | 150 once daily | N/A | N/A | 17 | 0.72 (0.61,0.85) | 0.72 (0.59,0.87) | N/A
Norgestimate/ ethinyl estradiol [Study conducted with STRIBILD.] | 0.180/0.215/ 0.250 norgestimate once daily | 150 once daily | 150 once daily | 200 once daily | N/A | 13 | 2.08 (2.00,2.17) | 2.26 (2.15,2.37) | 2.67 (2.43,2.92)
Norgestimate/ ethinyl estradiol [Study conducted with STRIBILD.] | 0.025 ethinyl estradiol once daily | 150 once daily | 150 once daily |  | N/A | 13 | 0.94 (0.86,1.04) | 0.75 (0.69,0.81) | 0.56 (0.52,0.61)
Norgestromin | 0.180/0.215/ 0.250 norgestimate once daily / 0.025 ethinyl estradiol once daily | N/A | N/A | 200 once daily [Study conducted with DESCOVY.] | 25 once daily | 15 | 1.17 (1.07,1.26) | 1.12 (1.07,1.17) | 1.16 (1.08,1.24)
Norgestrel | 0.180/0.215/ 0.250 norgestimate once daily / 0.025 ethinyl estradiol once daily | N/A | N/A | 200 once daily [Study conducted with DESCOVY.] | 25 once daily | 15 | 1.10 (1.02,1.18) | 1.09 (1.01,1.18) | 1.11 (1.03,1.20)
Ethinyl estradiol | 0.180/0.215/ 0.250 norgestimate once daily / 0.025 ethinyl estradiol once daily | N/A | N/A | 200 once daily [Study conducted with DESCOVY.] | 25 once daily | 15 | 1.22 (1.15,1.29) | 1.11 (1.07,1.16) | 1.02 (0.92,1.12)
R-Methadone | 80–120 daily | 150 once daily | 150 once daily | N/A | N/A | 11 | 1.01 (0.91,1.13) | 1.07 (0.96,1.19) | 1.10 (0.95,1.28)
S-Methadone | 80–120 daily | 150 once daily | 150 once daily | N/A | N/A | 11 | 0.96 (0.87,1.06) | 1.00 (0.89,1.12) | 1.02 (0.89,1.17)
Sertraline | 50 single dose | 150 once daily | 150 once daily | 200 once daily | 10 once daily | 19 | 1.14 (0.94,1.38) | 0.93 (0.77,1.13) | N/A
Rifabutin | 150 once every other day | 150 once daily | 150 once daily | N/A | N/A | 12 | 1.09 (0.98,1.20) [Comparison based on rifabutin 300 mg once daily.] | 0.92 (0.83,1.03) | 0.94 (0.85,1.04)
25-O-desacetyl-rifabutin | 150 once every other day | 150 once daily | 150 once daily | N/A | N/A | 12 | 4.84 (4.09,5.74) | 6.25 (5.08,7.69) | 4.94 (4.04,6.04)
Rosuvastatin | 10 single dose | 150 once daily | 150 once daily | N/A | N/A | 10 | 1.89 (1.48,2.42) | 1.38 (1.14,1.67) | NC
Sofosbuvir | 400 once daily | 150 once daily | 150 once daily | 200 once daily | 10 once daily | 24 | 1.23 (1.07,1.42) | 1.37 (1.24,1.52) | N/A
GS-331007 | 400 once daily | 150 once daily | 150 once daily | 200 once daily | 10 once daily | 24 | 1.29 (1.25,1.33) | 1.48 (1.43,1.53) | 1.58 (1.52,1.65)
Velpatasvir | 100 once daily | 150 once daily | 150 once daily | 200 once daily | 10 once daily | 24 | 1.30 (1.17,1.45) | 1.50 (1.35,1.66) | 1.60 (1.44,1.78)
Sofosbuvir | 400 once daily | 150 once daily | 150 once daily | 200 once daily | 10 once daily | 29 | 1.27 (1.09,1.48) | 1.22 (1.12,1.32) | NC
GS-331007 | 400 once daily | 150 once daily | 150 once daily | 200 once daily | 10 once daily | 29 | 1.28 (1.25,1.32) | 1.43 (1.39,1.47) | NC
Velpatasvir | 100 once daily | 150 once daily | 150 once daily | 200 once daily | 10 once daily | 29 | 0.96 (0.89,1.04) | 1.16 (1.06,1.27) | 1.46 (1.30,1.64)
Voxilaprevir | 100 + 100 [Study conducted with additional voxilaprevir 100 mg to achieve voxilaprevir exposures expected in HCV-infected patients.] once daily | 150 once daily | 150 once daily | 200 once daily | 10 once daily | 29 | 1.92 (1.63,2.26) | 2.71 (2.30,3.19) | 4.50 (3.68,5.50)
FTC = emtricitabine; TAF = tenofovir alafenamide
N/A = Not Applicable; NC = Not Calculated

12.4 Microbiology

Mechanism of Action

Elvitegravir: Elvitegravir inhibits the strand transfer activity of HIV-1 integrase (integrase strand transfer inhibitor; INSTI), an HIV-1 encoded enzyme that is required for viral replication. Inhibition of integrase prevents the integration of HIV-1 DNA into host genomic DNA, blocking the formation of the HIV-1 provirus and propagation of the viral infection. Elvitegravir does not inhibit human topoisomerases I or II.

Cobicistat: Cobicistat is a selective, mechanism-based inhibitor of cytochromes P450 of the CYP3A subfamily. Inhibition of CYP3A-mediated metabolism by cobicistat enhances the systemic exposure of CYP3A substrates, such as elvitegravir, where bioavailability is limited and half-life is shortened by CYP3A-dependent metabolism.

Emtricitabine: Emtricitabine, a synthetic nucleoside analog of cytidine, is phosphorylated by cellular enzymes to form emtricitabine 5'-triphosphate. Emtricitabine 5'-triphosphate inhibits the activity of the HIV-1 reverse transcriptase by competing with the natural substrate deoxycytidine 5'-triphosphate and by being incorporated into nascent viral DNA which results in chain termination. Emtricitabine 5'-triphosphate is a weak inhibitor of mammalian DNA polymerases α, β, Ɛ, and mitochondrial DNA polymerase γ.

Tenofovir Alafenamide (TAF): TAF is a phosphonamidate prodrug of tenofovir (2'-deoxyadenosine monophosphate analog). Plasma exposure to TAF allows for permeation into cells and then TAF is intracellularly converted to tenofovir through hydrolysis by cathepsin A. Tenofovir is subsequently phosphorylated by cellular kinases to the active metabolite tenofovir diphosphate. Tenofovir diphosphate inhibits HIV-1 replication through incorporation into viral DNA by the HIV reverse transcriptase, which results in DNA chain-termination.

Tenofovir has activity that is specific to human immunodeficiency virus and hepatitis B virus. Cell culture studies have shown that both emtricitabine and tenofovir can be fully phosphorylated when combined in cells. Tenofovir diphosphate is a weak inhibitor of mammalian DNA polymerases that include mitochondrial DNA polymerase γ and there is no evidence of mitochondrial toxicity in cell culture based on several assays including mitochondrial DNA analyses.

Antiviral Activity in Cell Culture

Elvitegravir, Cobicistat, Emtricitabine, and Tenofovir Alafenamide (TAF): The combination of elvitegravir, emtricitabine, and TAF was not antagonistic in cell culture combination antiviral activity assays and was not affected by the addition of cobicistat. In addition, elvitegravir, cobicistat, emtricitabine, and TAF were not antagonistic with a panel of representatives from the major classes of approved anti-HIV-1 agents (INSTIs, NNRTIs, NRTIs, and PIs).

Elvitegravir: The antiviral activity of elvitegravir against laboratory and clinical isolates of HIV-1 was assessed in T lymphoblastoid cell lines, monocyte/macrophage cells, and primary peripheral blood lymphocytes. The 50% effective concentrations (EC50) ranged from 0.02 to 1.7 nM. Elvitegravir displayed antiviral activity in cell culture against HIV-1 clades A, B, C, D, E, F, G, and O (EC50 values ranged from 0.1 to 1.3 nM) and activity against HIV-2 (EC50 value of 0.53 nM). Elvitegravir did not show inhibition of replication of HBV or HCV in cell culture.

Cobicistat: Cobicistat has no detectable antiviral activity in cell culture against HIV-1, HBV, or HCV and does not antagonize the antiviral activity of elvitegravir, emtricitabine, or tenofovir.

Emtricitabine: The antiviral activity of emtricitabine against laboratory and clinical isolates of HIV-1 was assessed in T lymphoblastoid cell lines, the MAGI-CCR5 cell line, and primary peripheral blood mononuclear cells. The EC50 values for emtricitabine were in the range of 1.3 – 640 nM. Emtricitabine displayed antiviral activity in cell culture against HIV-1 clades A, B, C, D, E, F, and G (EC50 values ranged from 7–75 nM) and showed strain specific activity against HIV-2 (EC50 values ranged from 7–1500 nM).

Tenofovir Alafenamide (TAF): The antiviral activity of TAF against laboratory and clinical isolates of HIV-1 subtype B was assessed in lymphoblastoid cell lines, PBMCs, primary monocyte/macrophage cells and CD4-T lymphocytes. The EC50 values for TAF ranged from 2.0 to 14.7 nM.

TAF displayed antiviral activity in cell culture against all HIV-1 groups (M, N, O), including sub-types A, B, C, D, E, F, and G (EC50 values ranged from 0.10 to 12.0 nM) and strain specific activity against HIV-2 (EC50 values ranged from 0.91 to 2.63 nM).

Resistance

In Cell Culture

Elvitegravir: HIV-1 isolates with reduced susceptibility to elvitegravir have been selected in cell culture. Reduced susceptibility to elvitegravir was associated with the primary integrase substitutions T66A/I, E92G/Q, S147G, and Q148R. Additional integrase substitutions observed in cell culture selection included D10E, S17N, H51Y, F121Y, S153F/Y, E157Q, D232N, R263K, and V281M.

Emtricitabine: HIV-1 isolates with reduced susceptibility to emtricitabine have been selected in cell culture. Reduced susceptibility to emtricitabine was associated with M184V or I substitutions in HIV-1 RT.

Tenofovir Alafenamide (TAF): HIV-1 isolates with reduced susceptibility to TAF have been selected in cell culture. HIV-1 isolates selected by TAF expressed a K65R substitution in HIV-1 RT, sometimes in the presence of S68N or L429I substitutions; in addition, a K70E substitution in HIV-1 RT was observed.

In Clinical Trials

In Treatment-Naïve Subjects:

In a pooled analysis of antiretroviral-naïve subjects receiving GENVOYA in Studies 104 and 111, genotyping was performed on plasma HIV-1 isolates from all subjects with HIV-1 RNA greater than 400 copies per mL at confirmed virologic failure, at Week 144, or at time of early study drug discontinuation. As of Week 144, the development of genotypic resistance to elvitegravir, emtricitabine, or TAF was observed in 12 of 22 subjects with evaluable resistance data from paired baseline and GENVOYA treatment-failure isolates (12 of 866 subjects [1.4%]) compared with 13 of 20 treatment-failure isolates from subjects with evaluable resistance data in the STRIBILD treatment group (13 of 867 subjects [1.5%]). Of the 12 subjects with resistance development in the GENVOYA group, the resistance-associated substitutions that emerged were M184V/I (N=11) and K65R/N (N=2) in reverse transcriptase and T66T/A/I/V (N=2), E92Q (N=4), E138K (N=1), Q148Q/R (N=1) and N155H (N=2) in integrase. Of the 13 subjects with resistance development in the STRIBILD group, the resistance-associated substitutions that emerged were M184V/I (N=9), K65R/N (N=4), and L210W (N=1) in reverse transcriptase and E92Q/V (N=4), E138K (N=3), Q148R (N=2), and N155H/S (N=3) in integrase. In both treatment groups, most subjects who developed substitutions associated with resistance to elvitegravir also developed emtricitabine resistance-associated substitutions. These genotypic resistance results were confirmed by phenotypic analyses.

In Virologically Suppressed Subjects:

Three virologic failure subjects were identified with emergent genotypic and phenotypic resistance to GENVOYA (all three with M184I or V and one with K219Q in reverse transcriptase; two with E92Q or G in integrase) out of 8 virologic failure subjects with resistance data in a clinical study of virologically-suppressed subjects who switched from a regimen containing emtricitabine/TDF and a third agent to GENVOYA (Study 109, N=959).

Cross-Resistance

No cross-resistance has been demonstrated for elvitegravir-resistant HIV-1 isolates and emtricitabine or tenofovir, or for emtricitabine- or tenofovir-resistant isolates and elvitegravir.

Elvitegravir: Cross-resistance has been observed among INSTIs. Elvitegravir-resistant viruses showed varying degrees of cross-resistance in cell culture to raltegravir depending on the type and number of amino acid substitutions in HIV-1 integrase. Of the primary elvitegravir resistance-associated substitutions tested (T66A/I/K, E92G/Q, T97A, S147G, Q148H/K/R, and N155H), all but three (T66I, E92G, and S147G) conferred greater than 1.5-fold reduced susceptibility to raltegravir (above the biological cutoff for raltegravir) when introduced individually into a wild-type virus by site-directed mutagenesis. Of the primary raltegravir resistance-associated substitutions (Y143C/H/R, Q148H/K/R, and N155H), all but Y143C/H conferred greater than 2.5-fold reductions in susceptibility to elvitegravir (above the biological cutoff for elvitegravir). Some viruses expressing elvitegravir or raltegravir resistance amino acid substitutions maintain susceptibility to dolutegravir.

Emtricitabine: Cross-resistance has been observed among NRTIs. Emtricitabine-resistant isolates harboring an M184V/I substitution in HIV-1 RT were cross-resistant to lamivudine. HIV-1 isolates containing the K65R RT substitution, selected in vivo by abacavir, didanosine, and tenofovir, demonstrated reduced susceptibility to inhibition by emtricitabine.

Tenofovir Alafenamide (TAF): Tenofovir resistance substitutions, K65R and K70E, result in reduced susceptibility to abacavir, didanosine, emtricitabine, lamivudine, and tenofovir.

HIV-1 with multiple TAMs (M41L, D67N, K70R, L210W, T215F/Y, K219Q/E/N/R), or multinucleoside resistant HIV-1 with a T69S double insertion mutation or with a Q151M mutation complex including K65R, showed reduced susceptibility to TAF in cell culture.

13 NONCLINICAL TOXICOLOGY

13.1 Carcinogenesis, Mutagenesis, Impairment of Fertility

Elvitegravir

Long-term carcinogenicity studies of elvitegravir were carried out in mice (104 weeks) and in rats for up to 88 weeks (males) and 90 weeks (females). No drug-related increases in tumor incidence were found in mice at doses up to 2000 mg per kg per day alone or in combination with 25 mg per kg per day RTV at exposures 3- and 14 times, respectively, the human systemic exposure at the recommended daily dose of 150 mg. No drug-related increases in tumor incidence were found in rats at doses up to 2000 mg per kg per day at exposures 12- to 27 times, respectively in male and female, the human systemic exposure.

Elvitegravir was not genotoxic in the reverse mutation bacterial test (Ames test) and the rat micronucleus assay. In an in vitro chromosomal aberration test, elvitegravir was negative with metabolic activation; however, an equivocal response was observed without activation.

Elvitegravir did not affect fertility in male and female rats at approximately 16- and 30 times higher exposures (AUC), respectively, than in humans at the recommended 150 mg daily dose.

Fertility was normal in the offspring of rats exposed daily from before birth (in utero) through sexual maturity at daily exposures (AUC) of approximately 18 times higher than human exposures at the recommended 150 mg daily dose.

Cobicistat

In a long-term carcinogenicity study in mice, no drug-related increases in tumor incidence were observed at doses up to 50 and 100 mg/kg/day (males and females, respectively). Cobicistat exposures at these doses were approximately 7 (male) and 16 (females) times, respectively, the human systemic exposure at the therapeutic daily dose. In a long-term carcinogenicity study of cobicistat in rats, an increased incidence of follicular cell adenomas and/or carcinomas in the thyroid gland was observed at doses of 25 and 50 mg/kg/day in males, and at 30 mg/kg/day in females. The follicular cell findings are considered to be rat-specific, secondary to hepatic microsomal enzyme induction and thyroid hormone imbalance, and are not relevant for humans. At the highest doses tested in the rat carcinogenicity study, systemic exposures were approximately 2 times the human systemic exposure at the recommended daily dose.

Cobicistat was not genotoxic in the reverse mutation bacterial test (Ames test), mouse lymphoma or rat micronucleus assays.

Cobicistat did not affect fertility in male or female rats at daily exposures (AUC) approximately 4 times higher than human exposures at the recommended 150 mg daily dose.

Fertility was normal in the offspring of rats exposed daily from before birth (in utero) through sexual maturity at daily exposures (AUC) of approximately 1.2 times higher than human exposures at the recommended 150 mg daily dose.

Emtricitabine

In long-term carcinogenicity studies of emtricitabine, no drug-related increases in tumor incidence were found in mice at doses up to 750 mg per kg per day (23 times the human systemic exposure at the therapeutic dose of 200 mg per day) or in rats at doses up to 600 mg per kg per day (28 times the human systemic exposure at the recommended dose).

Emtricitabine was not genotoxic in the reverse mutation bacterial test (Ames test), mouse lymphoma or mouse micronucleus assays.

Emtricitabine did not affect fertility in male rats at approximately 140 times or in male and female mice at approximately 60 times higher exposures (AUC) than in humans given the recommended 200 mg daily dose. Fertility was normal in the offspring of mice exposed daily from before birth (in utero) through sexual maturity at daily exposures (AUC) of approximately 60 times higher than human exposures at the recommended 200 mg daily dose.

Tenofovir Alafenamide (TAF)

Since TAF is rapidly converted to tenofovir and a lower tenofovir exposure in rats and mice is observed after TAF administration compared to TDF administration, carcinogenicity studies were conducted only with TDF. Long-term oral carcinogenicity studies of TDF in mice and rats were carried out at exposures up to approximately 10 times (mice) and 4 times (rats) those observed in humans at the 300 mg therapeutic dose of TDF for HIV-1 infection. The tenofovir exposure in these studies was approximately 167 times (mice) and 55 times (rat) those observed in humans after administration of GENVOYA treatment. At the high dose in female mice, liver adenomas were increased at tenofovir exposures 10 times (300 mg TDF) and 167 times (10 mg TAF in GENVOYA) that in humans. In rats, the study was negative for carcinogenic findings.

TAF was not genotoxic in the reverse mutation bacterial test (Ames test), mouse lymphoma or rat micronucleus assays.

There were no effects on fertility, mating performance or early embryonic development when TAF was administered to male rats at a dose equivalent to 155 times the human dose based on body surface area comparisons for 28 days prior to mating and to female rats for 14 days prior to mating through Day 7 of gestation.

13.2 Animal Toxicology and/or Pharmacology

Minimal to slight infiltration of mononuclear cells in the posterior uvea was observed in dogs with similar severity after three and nine month administration of TAF; reversibility was seen after a three month recovery period. At the NOAEL for eye toxicity, the systemic exposure in dogs was 5 (TAF) and 15 (tenofovir) times the exposure seen in humans at the recommended daily GENVOYA dosage.

14 CLINICAL STUDIES

14.1 Description of Clinical Trials

The efficacy and safety of GENVOYA were evaluated in the studies summarized in Table 15.

Table 15 Trials Conducted with GENVOYA in Subjects with HIV-1 Infection
Trial | Population | Study Arms (N) | Timepoint (Week)
Study 104 [Randomized, double blind, active controlled trial.] Study 111 | Treatment-naïve adults | GENVOYA (866) STRIBILD (867) | 144
Study 109 [Randomized, open label, active controlled trial.] | Virologically-suppressed [HIV-1 RNA less than 50 copies per mL.] adults | GENVOYA (959) ATRIPLA® or TRUVADA®+atazanavir+cobicistat or ritonavir or STRIBILD (477) | 96
Study 112 [Open label trial.] | Virologically-suppressed adults with renal impairment [Estimated creatinine clearance between 30 and 69 mL per minute by Cockcroft-Gault method.] | GENVOYA (242) | 144
Study 1825 | Virologically-suppressed adults with ESRD [End stage renal disease (estimated creatinine clearance of less than 15 mL per minute by Cockcroft-Gault method).] receiving chronic hemodialysis | GENVOYA (55) | 48
Study 106 (cohort 1) | Treatment-naïve adolescents between the ages of 12 to less than 18 years (at least 35 kg) | GENVOYA (50) | 48
Study 106 (cohort 2) | Virologically-suppressed children between the ages of 6 to less than 12 years (at least 25 kg) | GENVOYA (52) | 48

14.2 Clinical Trial Results in HIV-1 Treatment-Naïve Subjects

In both Study 104 and Study 111, subjects were randomized in a 1:1 ratio to receive either GENVOYA (N=866) once daily or STRIBILD (elvitegravir 150 mg, cobicistat 150 mg, emtricitabine 200 mg, TDF 300 mg) (N=867) once daily. The mean age was 36 years (range 18–76), 85% were male, 57% were White, 25% were Black, and 10% were Asian. Nineteen percent of subjects identified as Hispanic/Latino. The mean baseline plasma HIV-1 RNA was 4.5 log10 copies per mL (range 1.3–7.0) and 23% of subjects had baseline viral loads greater than 100,000 copies per mL. The mean baseline CD4+ cell count was 427 cells per mm^3 (range 0–1360) and 13% had CD4+ cell counts less than 200 cells per mm^3.

Pooled treatment outcomes of Studies 104 and 111 through Week 144 are presented in Table 16.

Table 16 Pooled Virologic Outcomes of Randomized Treatment in Studies 104 and 111 at Week 144 [Week 144 window was between Day 966 and 1049 (inclusive).] in Treatment-Naïve Subjects
 | GENVOYA (N=866) | STRIBILD (N=867)
HIV-1 RNA < 50 copies/mL [The primary endpoint was assessed at Week 48 and the virologic success rate was 92% in the GENVOYA group and 90% in the STRIBILD group, with a treatment difference of 2.0% (95% CI: -0.7% to 4.7%). The difference at Week 144 was primarily driven by discontinuations due to other reasons with last available HIV-1 RNA <50 copies/mL.] | 84% | 80%
HIV-1 RNA ≥ 50 copies/mL [Included subjects who had ≥50 copies/mL in the Week 144 window; subjects who discontinued early due to lack or loss of efficacy; subjects who discontinued for reasons other than an adverse event (AE), death or lack or loss of efficacy and at the time of discontinuation had a viral value of ≥ 50 copies/mL.] | 5% | 4%
No Virologic Data at Week 144 Window | 11% | 16%
Discontinued Study Drug Due to AE or Death [Includes subjects who discontinued due to AE or death at any time point from Day 1 through the time window if this resulted in no virologic data on treatment during the specified window.] | 2% | 3%
Discontinued Study Drug Due to Other Reasons and Last Available HIV-1 RNA < 50 copies/mL [Includes subjects who discontinued for reasons other than an AE, death or lack or loss of efficacy; e.g., withdrew consent, loss to follow-up, etc.] | 9% | 11%
Missing Data During Window but on Study Drug | 1% | 1%

Treatment outcomes were similar across subgroups by age, sex, race, baseline viral load, and baseline CD4+ cell count.

In Studies 104 and 111, the mean increase from baseline in CD4+ cell count at Week 144 was 326 cells per mm^3 in GENVOYA-treated subjects and 305 cells per mm^3 in STRIBILD-treated subjects.

14.3 Clinical Trial Results in HIV-1 Virologically-Suppressed Adults Who Switched to GENVOYA

In Study 109, the efficacy and safety of switching from ATRIPLA, TRUVADA plus atazanavir (given with either cobicistat or ritonavir), or STRIBILD to GENVOYA once daily were evaluated in a randomized, open-label trial of virologically-suppressed (HIV-1 RNA less than 50 copies per mL) HIV-1 infected adults (N=1436). Subjects must have been suppressed (HIV-1 RNA less than 50 copies per mL) on their baseline regimen for at least 6 months and had no known resistance-associated substitutions to any of the components of GENVOYA prior to study entry. Subjects were randomized in a 2:1 ratio to either switch to GENVOYA at baseline (N=959), or stay on their baseline antiretroviral regimen (N=477). Subjects had a mean age of 41 years (range 21–77), 89% were male, 67% were White, and 19% were Black. The mean baseline CD4+ cell count was 697 cells per mm^3 (range 79–1951).

Subjects were stratified by prior treatment regimen. At screening, 42% of subjects were receiving TRUVADA plus atazanavir (given with either cobicistat or ritonavir), 32% were receiving STRIBILD, and 26% were receiving ATRIPLA.

Treatment outcomes of Study 109 through 96 weeks are presented in Table 17.

Table 17 Virologic Outcomes of Study 109 at Week 96 [Week 96 window was between Day 630 and 713 (inclusive).] in Virologically-Suppressed Adults who Switched to GENVOYA
 | GENVOYA (N=959) | ATRIPLA or TRUVADA+atazanavir +cobicistat or ritonavir or STRIBILD (N=477)
HIV-1 RNA < 50 copies/mL | 93% | 89%
HIV-1 RNA ≥ 50 copies/mL [Included subjects who had ≥50 copies/mL in the Week 96 window; subjects who discontinued early due to lack or loss of efficacy; subjects who discontinued for reasons other than an adverse event (AE), death or lack or loss of efficacy and at the time of discontinuation had a viral value of ≥50 copies/mL.] | 2% | 2%
No Virologic Data at Week 48 Window | 5% | 9%
Discontinued Study Drug Due to AE or Death [Includes subjects who discontinued due to AE or death at any time point from Day 1 through the time window if this resulted in no virologic data on treatment during the specified window.] | 1% | 3%
Discontinued Study Drug Due to Other Reasons and Last Available HIV-1 RNA < 50 copies/mL [Includes subjects who discontinued for reasons other than an AE, death or lack or loss of efficacy; e.g., withdrew consent, loss to follow-up, etc.] | 3% | 6%
Missing Data During Window but on Study Drug | 1% | <1%

Treatment outcomes were similar across subgroups receiving ATRIPLA, TRUVADA plus atazanavir (given with either cobicistat or ritonavir), or STRIBILD prior to randomization. In Study 109, the mean increase from baseline in CD4+ cell count at Week 96 was 60 cells per mm^3 in GENVOYA-treated subjects and 42 cells per mm^3 in subjects who stayed on their baseline regimen.

14.4 Clinical Trial Results in HIV-1 Infected Subjects with Renal Impairment

Study 112: Virologically-suppressed adults with renal impairment

In Study 112, the efficacy and safety of GENVOYA once daily were evaluated in an open-label clinical trial of 248 HIV-1 infected subjects with renal impairment (estimated creatinine clearance between 30 and 69 mL per minute by Cockcroft-Gault method). Of the 248 enrolled, 6 were treatment-naïve and 242 were virologically suppressed (HIV-1 RNA less than 50 copies per mL) for at least 6 months before switching to GENVOYA [see Use in Specific Populations (8.6) and Clinical Pharmacology (12.3)].

The mean age was 58 years (range 24–82), with 63 subjects (26%) who were 65 years of age or older. Seventy-nine percent were male, 63% were White, 18% were Black, and 14% were Asian. Thirteen percent of subjects identified as Hispanic/Latino. The mean baseline CD4+ cell count was 664 cells per mm^3 (range 126–1813). At Week 144, 81% (197/242 virologically suppressed subjects) maintained HIV-1 RNA less than 50 copies per mL after switching to GENVOYA. All six treatment-naïve subjects were virologically suppressed at Week 144. Five subjects among the entire study population had virologic failure at Week 144.

Study 1825: Virologically-suppressed adults with end stage renal disease (ESRD) receiving chronic hemodialysis

In Study 1825, the efficacy and safety of GENVOYA once daily were evaluated in an open-label clinical trial of 55 virologically-suppressed (HIV-1 RNA less than 50 copies per mL for at least 6 months before switching to GENVOYA) HIV-1 infected subjects with ESRD (estimated creatinine clearance of less than 15 mL per minute by Cockcroft-Gault method) receiving chronic hemodialysis for at least 6 months [see Use in Specific Populations (8.6) and Clinical Pharmacology (12.3)].

Subjects had a mean age of 48 years (range 23–64), 76% were male, 82% were Black, 18% were White, and 15% identified as Hispanic/Latino. The mean baseline CD4+ cell count was 545 cell per mm^3 (range 205–1473). At Week 48, 82% (45/55) maintained HIV-1 RNA less than 50 copies per mL after switching to GENVOYA. Two subjects had HIV-1 RNA ≥ 50 copies per mL by Week 48. Seven subjects discontinued the study drug due to AE or other reasons while suppressed. One subject did not have an HIV-1 RNA measurement at Week 48.

14.5 Clinical Trial Results in HIV-1 Infected Pediatric Subjects Between the Ages of 6 to Less than 18 Years

In Study 106, an open-label, single arm trial the efficacy, safety, and pharmacokinetics of GENVOYA in HIV-1 infected pediatric subjects were evaluated in treatment-naïve adolescents between the ages of 12 to less than 18 years weighing at least 35 kg (N=50) and in virologically-suppressed children between the ages of 6 to less than 12 years weighing at least 25 kg (N=52).

Cohort 1: Treatment-naïve adolescents (12 to less than 18 years; at least 35 kg)

Subjects in cohort 1 treated with GENVOYA once daily had a mean age of 15 years (range 12-17); 44% were male, 12% were Asian, and 88% were Black. At baseline, mean plasma HIV-1 RNA was 4.6 log10 copies per mL (22% had baseline plasma HIV-1 RNA greater than 100,000 copies per mL), mean (SD) CD4+ cell count was 471 (212.2) cells per mm^3, and mean (SD) CD4+ percentage was 23.6% (8.8%).

In subjects in cohort 1 treated with GENVOYA, 92% (46/50) achieved HIV-1 RNA less than 50 copies per mL at Week 48. The mean increase from baseline in CD4+ cell count at Week 48 was 224 cells per mm^3. Three of 50 subjects had virologic failure at Week 48; no emergent resistance to GENVOYA was detected through Week 48.

Cohort 2: Virologically-suppressed children (6 to less than 12 years; at least 25 kg)

Subjects in cohort 2 treated with GENVOYA once daily had a mean age of 10 years (range: 7–11), a mean baseline weight of 31.7 kg, 42% were male, 25% were Asian, and 71% were Black. At baseline, the mean (SD) CD4+ cell count was 961 (275.5) cells per mm^3 and the mean (SD) CD4 percentage was 38.2% (6.4%). After switching to GENVOYA, 98% (51/52) of subjects in cohort 2 remained suppressed (HIV-1 RNA < 50 copies/mL) at Week 48. No subject qualified for resistance analysis through Week 48. The mean change from baseline in CD4+ cell count was -66 (203.6) cells per mm^3 and the mean (SD) change in CD4 percentage was -0.6% (4.4%) at Week 48. All subjects maintained CD4+ cell counts above 400 cells/mm^3 [see Adverse Reactions (6.1) and Pediatric Use (8.4)].

16 HOW SUPPLIED/STORAGE AND HANDLING

GENVOYA tablets are available in bottles containing 30 tablets with a silica gel desiccant, polyester coil, and child-resistant closure as follows:

- GENVOYA tablets each contain 150 mg of elvitegravir (EVG), 150 mg of cobicistat (COBI), 200 mg of emtricitabine (FTC), and 10 mg of tenofovir alafenamide (TAF). These tablets are green, capsule-shaped, film-coated, debossed with "GSI" on one side of the tablet and the number "510" on the other side (NDC 61958-1901-1).

STORAGE AND HANDLING

Store below 30 °C (86 °F).

- Keep container tightly closed.
- Dispense only in original container.

17 PATIENT COUNSELING INFORMATION

Advise the patient to read the FDA-approved patient labeling (Patient Information).

Drug Interactions

GENVOYA may interact with many drugs; therefore, advise patients to report to their healthcare provider the use of any other prescription or non-prescription medication or herbal products including St. John's wort [see Contraindications (4) and Drug Interactions (7)].

Post-treatment Acute Exacerbation of Hepatitis B in Patients with HBV Co-Infection

Severe acute exacerbations of hepatitis B have been reported in patients who are coinfected with HBV and HIV-1 and have discontinued products containing emtricitabine and/or TDF, and may likewise occur with discontinuation of GENVOYA [see Warnings and Precautions (5.1)]. Advise the patient to not discontinue GENVOYA without first informing their healthcare provider.

Immune Reconstitution Syndrome

Advise patients to inform their healthcare provider immediately of any symptoms of infection, as in some patients with advanced HIV infection (AIDS), signs and symptoms of inflammation from previous infections may occur soon after anti-HIV treatment is started [see Warnings and Precautions (5.3)].

Renal Impairment

Advise patients to avoid taking GENVOYA with concurrent or recent use of nephrotoxic agents. Postmarketing cases of renal impairment, including acute renal failure, have been reported [see Warnings and Precautions (5.4)].

Lactic Acidosis and Severe Hepatomegaly

Lactic acidosis and severe hepatomegaly with steatosis, including fatal cases, have been reported with use of drugs similar to GENVOYA. Advise patients that they should stop GENVOYA if they develop clinical symptoms suggestive of lactic acidosis or pronounced hepatotoxicity [see Warnings and Precautions (5.5)].

Missed Dosage

Inform patients that it is important to take GENVOYA on a regular dosing schedule with food and to avoid missing doses as it can result in development of resistance [see Dosage and Administration (2.2)].

Pregnancy

Advise patients that GENVOYA is not recommended during pregnancy and to alert their healthcare provider if they become pregnant while taking GENVOYA [see Dosage and Administration (2.5) and Use in Specific Populations (8.1)]. Inform patients that there is an antiretroviral pregnancy registry to monitor fetal outcomes of pregnant individuals exposed to GENVOYA [see Use in Specific Populations (8.1)].

Lactation

Instruct patients with HIV-1 infection not to breastfeed because HIV-1 can be passed to the baby in breast milk [see Use in Specific Populations (8.2)].

Manufactured and distributed by: Gilead Sciences, Inc. Foster City, CA 94404

Patient Information

GENVOYA® (jen-VOY-uh)
(elvitegravir, cobicistat, emtricitabine,
and tenofovir alafenamide)
tablets

Important: Ask your healthcare provider or pharmacist about medicines that should not be taken with GENVOYA. For more information, see the section "What should I tell my healthcare provider before taking GENVOYA?"

What is the most important information I should know about GENVOYA?

GENVOYA can cause serious side effects, including:

- Worsening of hepatitis B virus (HBV) infection. Your healthcare provider will test you for HBV infection before or when you start treatment with GENVOYA. If you have HBV infection and take GENVOYA, your HBV may get worse (flare-up) if you stop taking GENVOYA. A "flare-up" is when your HBV infection suddenly returns in a worse way than before.
  - Do not run out of GENVOYA. Refill your prescription or talk to your healthcare provider before your GENVOYA is all gone.
  - Do not stop taking GENVOYA without first talking to your healthcare provider.
  - If you stop taking GENVOYA, your healthcare provider will need to check your health often and do blood tests regularly for several months to check your liver, and may give you a medicine to treat hepatitis B. Tell your healthcare provider about any new or unusual symptoms you may have after you stop taking GENVOYA.

For more information about side effects, see "What are the possible side effects of GENVOYA?"

What is GENVOYA?

GENVOYA is a prescription medicine that is used without other human immunodeficiency virus-1 (HIV-1) medicines to treat HIV-1 infection in adults and children who weigh at least 55 pounds (25 kg):

- who have not received HIV-1 medicines in the past, or
- to replace their current HIV-1 medicines for people whose healthcare provider determines that they meet certain requirements.

HIV-1 is the virus that causes Acquired Immune Deficiency Syndrome (AIDS).

GENVOYA contains the prescription medicines elvitegravir, cobicistat, emtricitabine and tenofovir alafenamide.

It is not known if GENVOYA is safe and effective in children who weigh less than 55 pounds (25 kg).

Do not take GENVOYA if you also take a medicine that contains:

- alfuzosin hydrochloride
- carbamazepine
- ergot-containing medicines, including:
  - dihydroergotamine mesylate
  - ergotamine tartrate
  - methylergonovine maleate
- lomitapide
- lovastatin
- lurasidone

- midazolam, when taken by mouth
- phenobarbital
- phenytoin
- pimozide
- rifampin
- sildenafil, when used for treating the lung problem, pulmonary arterial hypertension
- simvastatin
- triazolam

- St. John's wort (Hypericum perforatum) or a product that contains St. John's wort.

What should I tell my healthcare provider before taking GENVOYA?

Before taking GENVOYA, tell your healthcare provider about all of your medical conditions, including if you:

- have liver problems, including HBV infection
- have kidney problems
- are pregnant or plan to become pregnant.
  - It is not known if GENVOYA can harm your unborn baby.
  - GENVOYA should not be used during pregnancy because you may not have enough GENVOYA in your body during pregnancy.
  - Tell your healthcare provider if you become pregnant during treatment with GENVOYA. Your healthcare provider may prescribe different medicines if you become pregnant while taking GENVOYA.
  Pregnancy Registry: There is a pregnancy registry for women who take antiretroviral medicines during pregnancy. The purpose of this registry is to collect information about the health of you and your baby. Talk with your healthcare provider about how you can take part in this registry.
- are breastfeeding or plan to breastfeed. Do not breastfeed if you take GENVOYA.
  - You should not breastfeed if you have HIV-1 because of the risk of passing HIV-1 to your baby.
  - At least one of the medicines in GENVOYA can pass to your baby in your breast milk. It is not known if the other medicines in GENVOYA can pass into your breast milk.
  Talk with your healthcare provider about the best way to feed your baby during treatment with GENVOYA.

Tell your healthcare provider about all the medicines you take, including prescription and over-the-counter medicines, vitamins, and herbal supplements.

Some medicines may interact with GENVOYA. Keep a list of your medicines and show it to your healthcare provider and pharmacist when you get a new medicine.

- You can ask your healthcare provider or pharmacist for a list of medicines that interact with GENVOYA.
- Do not start a new medicine without telling your healthcare provider. Your healthcare provider can tell you if it is safe to take GENVOYA with other medicines.

How should I take GENVOYA?

- Take GENVOYA exactly as your healthcare provider tells you to take it. GENVOYA is taken by itself (not with other HIV-1 medicines) to treat HIV-1 infection.
- Take GENVOYA 1 time each day with food.
- If you are on dialysis, take your daily dose of GENVOYA following dialysis.
- Do not change your dose or stop taking GENVOYA without first talking with your healthcare provider. Stay under a healthcare provider's care during treatment with GENVOYA.
- If you need to take a medicine for indigestion (antacid) that contains aluminum hydroxide, magnesium hydroxide, or calcium carbonate during treatment with GENVOYA, take it at least 2 hours before or after you take GENVOYA.
- Do not miss a dose of GENVOYA.
- When your GENVOYA supply starts to run low, get more from your healthcare provider or pharmacy. This is very important because the amount of virus in your blood may increase if the medicine is stopped for even a short time. The virus may develop resistance to GENVOYA and become harder to treat.
- If you take too much GENVOYA, call your healthcare provider or go to the nearest hospital emergency room right away.

What are the possible side effects of GENVOYA?

GENVOYA may cause serious side effects, including:

- See "What is the most important information I should know about GENVOYA?"
- Changes in your immune system (Immune Reconstitution Syndrome) can happen when you start taking HIV-1 medicines. Your immune system may get stronger and begin to fight infections that have been hidden in your body for a long time. Tell your healthcare provider right away if you start having any new symptoms after starting your HIV-1 medicine.
- New or worse kidney problems, including kidney failure. Your healthcare provider should do blood and urine tests to check your kidneys when starting and during treatment with GENVOYA. Your healthcare provider may tell you to stop taking GENVOYA if you develop new or worse kidney problems.
- Too much lactic acid in your blood (lactic acidosis). Too much lactic acid is a serious but rare medical emergency that can lead to death. Tell your healthcare provider right away if you get these symptoms: weakness or being more tired than usual, unusual muscle pain, being short of breath or fast breathing, stomach pain with nausea and vomiting, cold or blue hands and feet, feel dizzy or lightheaded, or a fast or abnormal heartbeat.
- Severe liver problems. In rare cases, severe liver problems can happen that can lead to death. Tell your healthcare provider right away if you get these symptoms: skin or the white part of your eyes turns yellow, dark "tea-colored" urine, light-colored stools, loss of appetite for several days or longer, nausea, or stomach-area pain.

The most common side effect of GENVOYA is nausea.

These are not all the possible side effects of GENVOYA.

Call your doctor for medical advice about side effects. You may report side effects to FDA at 1-800-FDA-1088.

How should I store GENVOYA?

- Store GENVOYA below 86°F (30°C).
- Keep GENVOYA in its original container.
- Keep the container tightly closed.

Keep GENVOYA and all medicines out of reach of children.

General information about the safe and effective use of GENVOYA.

Medicines are sometimes prescribed for purposes other than those listed in a Patient Information leaflet. Do not use GENVOYA for a condition for which it was not prescribed. Do not give GENVOYA to other people, even if they have the same symptoms you have. It may harm them.

You can ask your healthcare provider or pharmacist for information about GENVOYA that is written for health professionals.

What are the ingredients in GENVOYA?

Active ingredients: elvitegravir, cobicistat, emtricitabine, and tenofovir alafenamide

Inactive ingredients: croscarmellose sodium, hydroxypropyl cellulose, lactose monohydrate, magnesium stearate, microcrystalline cellulose, silicon dioxide, and sodium lauryl sulfate. The tablets are film-coated with a coating material containing FD&C Blue No. 2/indigo carmine aluminum lake, iron oxide yellow, polyethylene glycol, polyvinyl alcohol, talc, and titanium dioxide.

Manufactured and distributed by: Gilead Sciences, Inc. Foster City, CA 94404

GENVOYA is a trademark of Gilead Sciences, Inc., or its related companies.

© 2022 Gilead Sciences, Inc. All rights reserved.

207561-GS--017

For more information, call 1-800-445-3235 or go to www.GENVOYA.com.

This Patient Information has been approved by the U.S. Food and Drug Administration

Revised: 01/2022

PRINCIPAL DISPLAY PANEL - 30 Tablet Bottle Label

NDC 61958-1901-1
30 tablets

Genvoya®
(elvitegravir, cobicistat,
emtricitabine, and tenofovir
alafenamide) Tablets
150 mg/150 mg/200 mg/10 mg

Note to pharmacist:
Do not cover ALERT box with pharmacy label.

ALERT: Find out about medicines that
should NOT be taken with Genvoya®